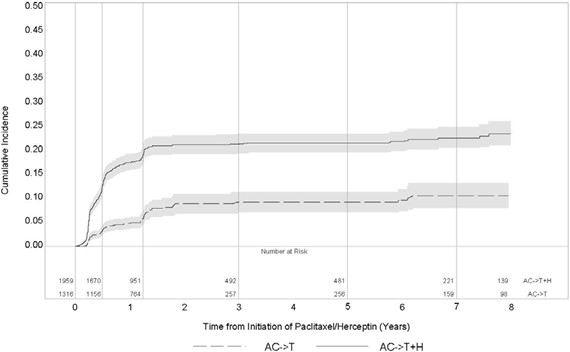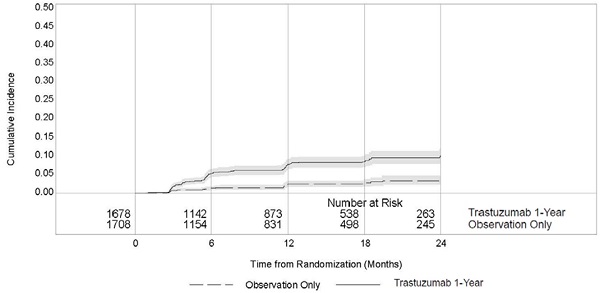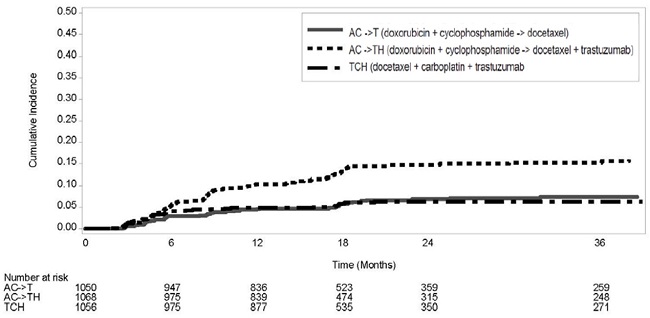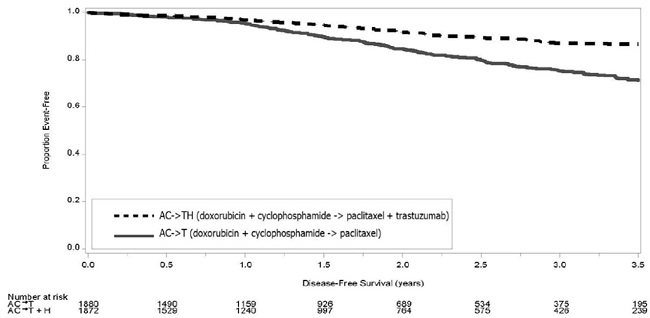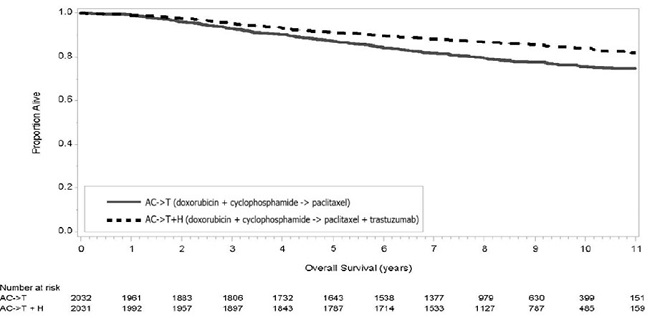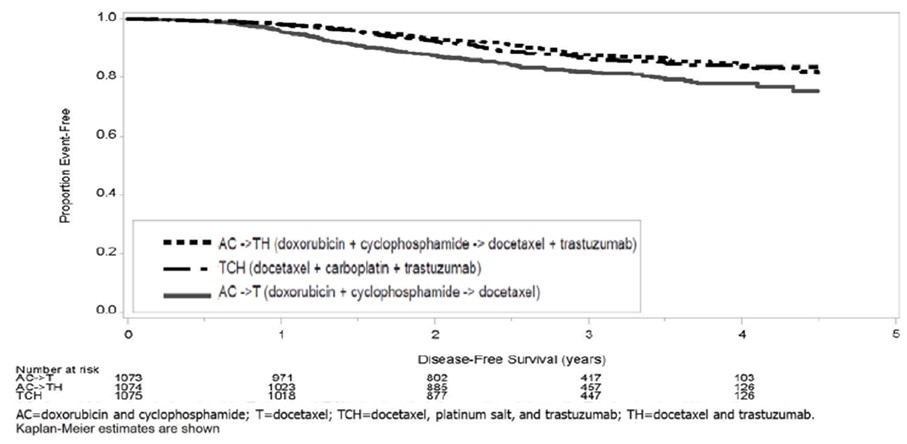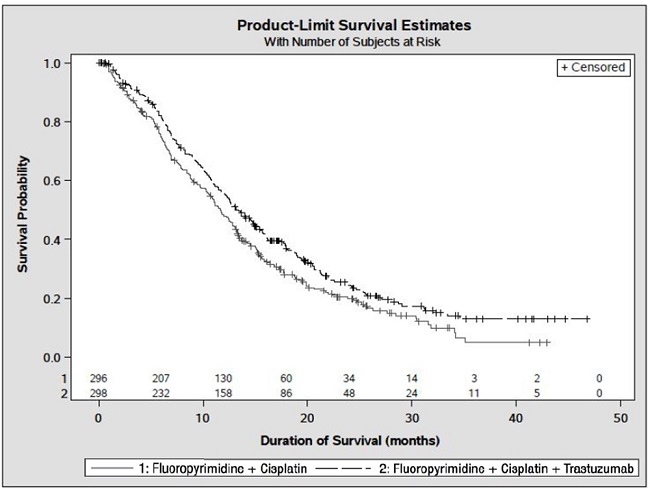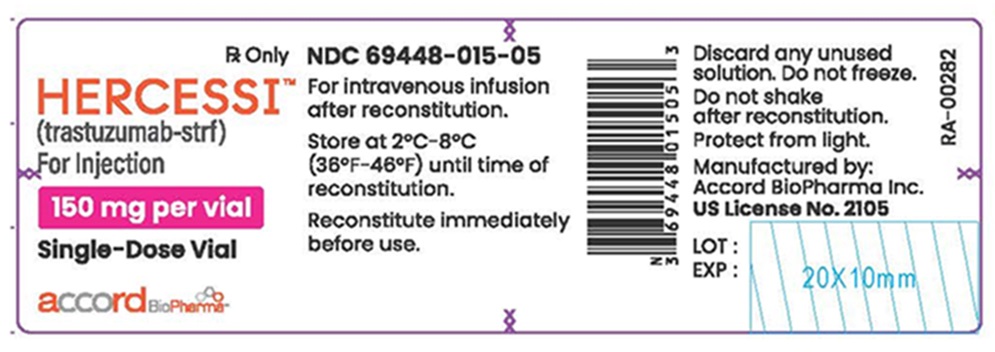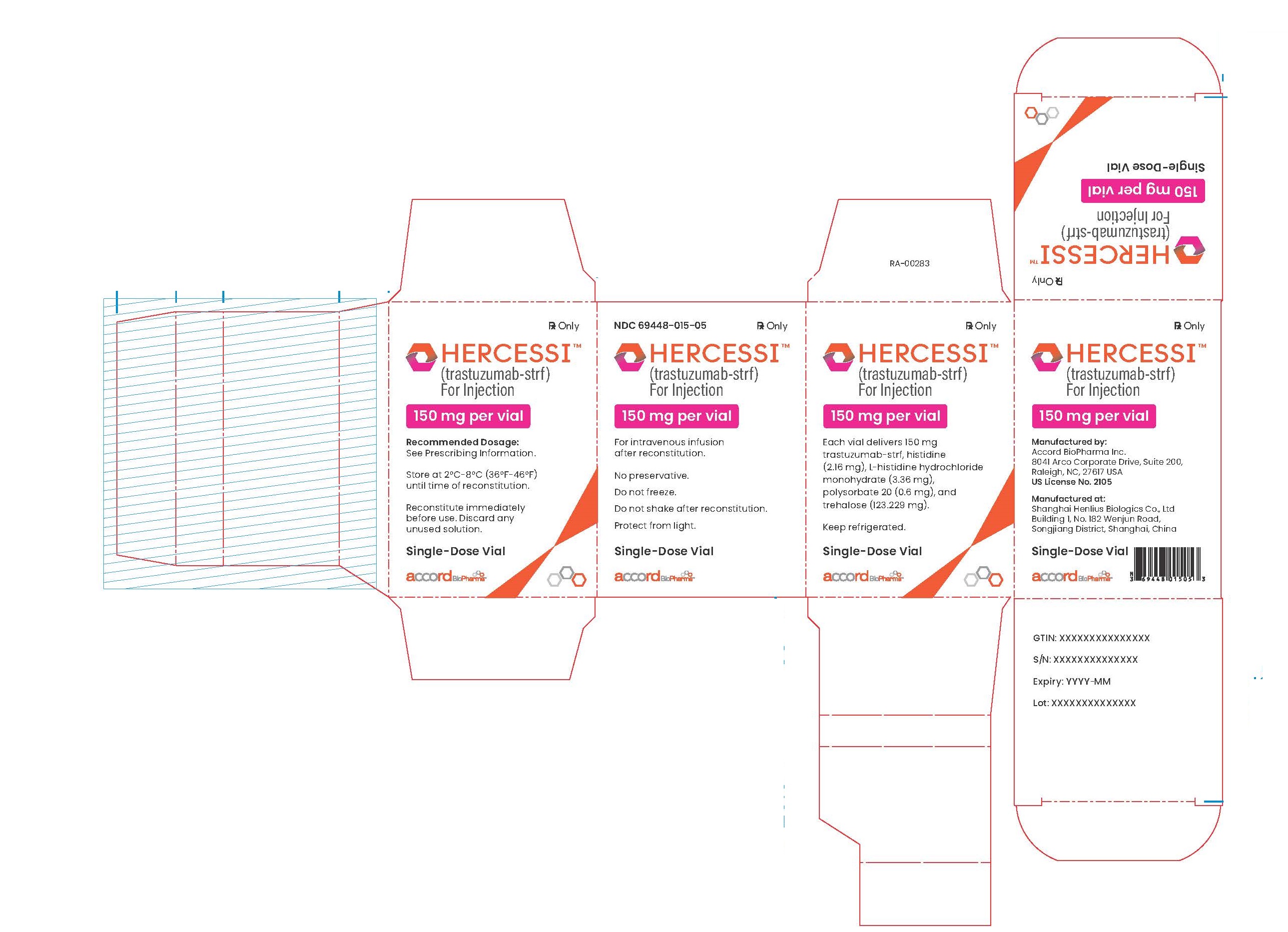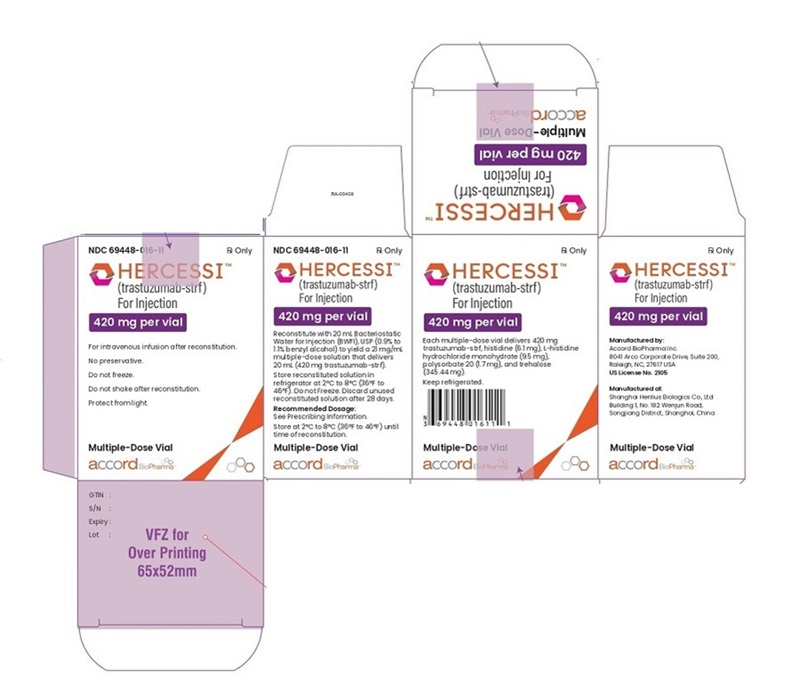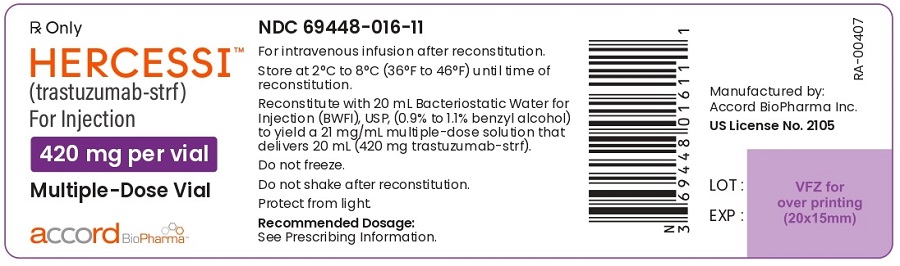 DRUG LABEL: HERCESSI
NDC: 69448-015 | Form: INJECTION, POWDER, LYOPHILIZED, FOR SOLUTION
Manufacturer: Accord BioPharma Inc.
Category: prescription | Type: HUMAN PRESCRIPTION DRUG LABEL
Date: 20250321

ACTIVE INGREDIENTS: TRASTUZUMAB 150 mg/7.4 mL
INACTIVE INGREDIENTS: HISTIDINE MONOHYDROCHLORIDE MONOHYDRATE 3.36 mg/7.4 mL; HISTIDINE 2.16 mg/7.4 mL; TREHALOSE DIHYDRATE 123.229 mg/7.4 mL; POLYSORBATE 20 0.6 mg/7.4 mL

HIGHLIGHTS OF PRESCRIBING INFORMATION

These highlights do not include all the information needed to use HERCESSI safely and effectively. See full prescribing information for HERCESSI.
HERCESSITM(trastuzumab-strf) for injection, for intravenous use
Initial U.S. Approval: 2024
HERCESSI (trastuzumab-strf) is biosimilar* to HERCEPTIN
(trastuzumab).

WARNING: CARDIOMYOPATHY, INFUSION REACTIONS, EMBRYO-FETAL TOXICITY, and PULMONARY TOXICITY See full prescribing information for complete boxed warning Cardiomyopathy: Trastuzumab products can result in subclinical and clinical cardiac failure manifesting as CHF, and decreased LVEF, with greatest risk when administered concurrently with anthracyclines. Evaluate cardiac function prior to and during treatment. Discontinue Hercessi for cardiomyopathy. (2.3, 5.1)Infusion Reactions, Pulmonary Toxicity: Discontinue Hercessi for anaphylaxis, angioedema, interstitial pneumonitis, or acute respiratory distress syndrome. (5.2, 5.4)Embryo-Fetal Toxicity: Exposure to trastuzumab products during pregnancy can result in oligohydramnios, in some cases complicated by pulmonary hypoplasia and neonatal death. Advise patients of these risks and the need for effective contraception. (5.3, 8.1, 8.3)

1 INDICATIONS AND USAGE

Hercessi is a HER2/neu receptor antagonist indicated for:

- The treatment of HER2-overexpressing breast cancer. (1.1,1.2)
- The treatment of HER2-overexpressing metastatic gastric or gastroesophageal junction adenocarcinoma. (1.3)

Select patients for therapy based on an FDA-approved companion diagnostic for a trastuzumab product (1,2.1).

2 DOSAGE AND ADMINISTRATION

For intravenous (IV) infusion only. Do not administer as an IV push or bolus. HERCESSITMhas different dosage and administration instructions than subcutaneous trastuzumab products. (2.3)
Do not substitute HERCESSITM(trastuzumab-strf) for or with ado-trastuzumab emtansine or fam-trastuzumab deruxtecan. (2.3)
Perform HER2 testing using FDA-approved tests by laboratories with demonstrated proficiency. (1,2.2)
Adjuvant Treatment of HER2-Overexpressing Breast Cancer (2.2)
Administer at either:
• Initial dose of 4 mg/kg over 90 minutes IV infusion, then 2 mg/kg over
30 minutes IV infusion weekly for 12 weeks (with paclitaxel or docetaxel) or 18 weeks (with docetaxel and carboplatin). One week after the last weekly dose of HERCESSITM, administer 6 mg/kg as an IV infusion over 30-90 minutes every three weeks to complete a total of 52 weeks of therapy, or
• Initial dose of 8 mg/kg over 90 minutes IV infusion, then 6 mg/kg over 30-90 minutes IV infusion every three weeks for 52 weeks.
Metastatic HER2-Overexpressing Breast Cancer (2.3)
• Initial dose of 4 mg/kg as a 90 minutes IV infusion followed by subsequent weekly doses of 2 mg/kg as 30 minutes IV infusions.
Metastatic HER2-Overexpressing Gastric Cancer (2.3)
• Initial dose of 8 mg/kg over 90 minutes IV infusion, followed by 6 mg/kg over 30 to 90 minutes IV infusion every 3 weeks.

3 DOSAGE FORMS AND STRENGTHS

• For Injection: 150 mg lyophilized powder in a single-dose vial for reconstitution
• For Injection: 420 mg lyophilized powder in a multiple-dose vial for reconstitution

4 CONTRAINDICATIONS

- None. (4)

5 WARNINGS AND PRECAUTIONS

- Exacerbation of Chemotherapy-Induced Neutropenia. (5.5, 6.1)

6 ADVERSE REACTIONS

Adjuvant Breast Cancer

- Most common adverse reactions (≥ 5%) are headache, diarrhea, nausea, and chills. (6.1)

Metastatic Breast Cancer

- Most common adverse reactions (≥ 10%) are fever, chills, headache, infection, congestive heart failure, insomnia, cough, and rash. (6.1)

Metastatic Gastric Cancer

- Most common adverse reactions (≥ 10%) are neutropenia, diarrhea, fatigue, anemia, stomatitis, weight loss, upper respiratory tract infections, fever, thrombocytopenia, mucosal inflammation, nasopharyngitis, and dysgeusia. (6.1)

To report SUSPECTED ADVERSE REACTIONS, contact Accord BioPharma Inc. at 1-866-941-7875 or FDA at 1-800-FDA-1088 or www.fda.gov/medwatch.

8 USE IN SPECIFIC POPULATIONS

Females and Males of Reproductive Potential: Verify the pregnancy status of females prior to initiation of Hercessi (8.3).
*Biosimilar means that the biological product is approved based on data demonstrating that it is highly similar to an FDA-approved biological product, known as a reference product, and that there are no clinically meaningful differences between the biosimilar product and the reference product. Biosimilarity of Hercessi has been demonstrated for the condition(s) of use (e.g. indication(s), dosing regimen(s)), strength(s), dosage form(s), and route(s) of administration described in its Full Prescribing Information.

FULL PRESCRIBING INFORMATION

WARNING: CARDIOMYOPATHY, INFUSION REACTIONS, EMBRYO-FETAL TOXICITY, and PULMONARY TOXICITY

Cardiomyopathy
Administration of trastuzumab products can result in sub-clinical and clinical cardiac failure. The incidence and severity was highest in patients receiving trastuzumab with anthracycline-containing chemotherapy regimens.
Evaluate left ventricular function in all patients prior to and during treatment with HERCESSITM. Discontinue HERCESSITMtreatment in patients receiving adjuvant therapy and withhold HERCESSITMin patients with metastatic disease for clinically significant decrease in left ventricular function [see Dosage and Administration (2.5) and Warnings and Precautions (5.1)].

Infusion Reactions; Pulmonary Toxicity
Administration of trastuzumab products can result in serious and fatal infusion reactions and pulmonary toxicity. Symptoms usually occur during or within 24 hours of administration of trastuzumab products. Interrupt HERCESSITMinfusion for dyspnea or clinically significant hypotension. Monitor patients until symptoms completely resolve. Discontinue HERCESSITMfor anaphylaxis, angioedema, interstitial pneumonitis, or acute respiratory distress syndrome [see Warnings and Precautions (5.2, 5.4)].

Embryo-Fetal Toxicity
Exposure to trastuzumab products during pregnancy can result in oligohydramnios and oligohydramnios sequence manifesting as pulmonary hypoplasia, skeletal abnormalities, and neonatal death. Advise patients of these risks and the need for effective contraception [see Warnings and Precautions (5.3)and Use in Specific Populations (8.1, 8.3)].

1 INDICATIONS AND USAGE

1.1 Adjuvant Breast Cancer

HERCESSITM is indicated for adjuvant treatment of HER2 overexpressing node positive or node negative (ER/PR negative or with one high risk feature [see Clinical Studies (14.1)])breast cancer

- as part of a treatment regimen consisting of doxorubicin, cyclophosphamide, and either paclitaxel or docetaxel
- as part of a treatment regimen with docetaxel and carboplatin
- as a single agent following multi-modality anthracycline based therapy.

Select patients for therapy based on an FDA-approved companion diagnostic for a trastuzumab product [see Dosage and Administration (2.2)].

1.2 Metastatic Breast Cancer

HERCESSITM is indicated:

- In combination with paclitaxel for first-line treatment of HER2-overexpressing metastatic breast cancer
- As a single agent for treatment of HER2-overexpressing breast cancer in patients who have received one or more chemotherapy regimens for metastatic disease.

Select patients for therapy based on an FDA-approved companion diagnostic for a trastuzumab product [see Dosage and Administration (2.1)].

1.3 Metastatic Gastric Cancer

HERCESSITM is indicated, in combination with cisplatin and capecitabine or 5-fluorouracil, for the treatment of patients with HER2-overexpressing metastatic gastric or gastroesophageal junction adenocarcinoma who have not received prior treatment for metastatic disease.

Select patients for therapy based on an FDA-approved companion diagnostic for a trastuzumab product [see Dosage and Administration (2.1)].

2 DOSAGE AND ADMINISTRATION

2.1 Evaluation and Testing Before Initiating HERCESSITM

Assess left ventricular ejection fraction (LVEF) prior to initiation of HERCESSITMand at regular intervals during treatment [see Boxed Warning, Dosage and Administration (2.5), Warnings and Precautions (5.1)].

Verify the pregnancy status of females of reproductive potential prior to the initiation of HERCESSITM [see Warnings and Precautions (5.3), Use in Specific Populations (8.1, 8.3)].

2.2 Patient Selection

Select patients based on HER2 protein overexpression or HER2 gene amplification in tumor specimens [see Indications and Usage (1) and Clinical Studies (14)]. Assessment of HER2 protein overexpression and HER2 gene amplification should be performed using FDA-approved tests specific for breast or gastric cancers by laboratories with demonstrated proficiency. Information on the FDA-approved tests for the detection of HER2 protein overexpression and HER2 gene amplification is available at: http://www.fda.gov/CompanionDiagnostics.

Assessment of HER2 protein overexpression and HER2 gene amplification in metastatic gastric cancer should be performed using FDA-approved tests specifically for gastric cancers due to differences in gastric vs. breast histopathology, including incomplete membrane staining and more frequent heterogeneous expression of HER2 seen in gastric cancers.

Improper assay performance, including use of suboptimally fixed tissue, failure to utilize specified reagents, deviation from specific assay instructions, and failure to include appropriate controls for assay validation, can lead to unreliable results.

2.3 Recommended Dosage

HERCESSITMis for intravenous infusion only. Do not administer as an intravenous push or bolus.
HERCESSITMhas different dosage and administration instructions than subcutaneous trastuzumab products.
Do not mix HERCESSITMwith other drugs.
Do not substitute HERCESSITM(trastuzumab-strf) for or with ado-trastuzumab emtansine or fam-trastuzumab deruxtecan.

Adjuvant Treatment, Breast Cancer

Administer according to one of the following doses and schedules for a total of 52 weeks of Hercessi therapy:

During and following paclitaxel, docetaxel, or docetaxel and carboplatin:

- Initial dose of 4 mg/kg as an intravenous infusion over 90 minutes then at 2 mg/kg as an intravenous infusion over 30 minutes weekly during chemotherapy for the first 12 weeks (paclitaxel or docetaxel) or 18 weeks (docetaxel and carboplatin).
- One week following the last weekly dose of Hercessi, administer Hercessi at 6 mg/kg as an intravenous infusion over 30-90 minutes every three weeks.

As a single agent within three weeks following completion of multi-modality, anthracycline-based chemotherapy regimens:

- Initial dose at 8 mg/kg as an intravenous infusion over 90 minutes
- Subsequent doses at 6 mg/kg as an intravenous infusion over 30-90 minutes every three weeks [see Dosage and Administration (2.3)].
- Extending adjuvant treatment beyond one year is not recommended [see Adverse Reactions (6.1)].

Metastatic Treatment, Breast Cancer

- Administer Hercessi, alone or in combination with paclitaxel, at an initial dose of 4 mg/kg as a 90-minute intravenous infusion followed by subsequent once weekly doses of 2 mg/kg as 30-minute intravenous infusions until disease progression.

Metastatic Gastric Cancer

- Administer Hercessi at an initial dose of 8 mg/kg as a 90-minute intravenous infusion followed by subsequent doses of 6 mg/kg as an intravenous infusion over 30–90 minutes every three weeks until disease progression (see Dosage and Administration2.3)].

2.4 Important Dosing Considerations

Missed Dose

If the patient has missed a dose of HERCESSITMby one week or less, then the usual maintenance dose (weekly schedule: 2 mg/kg; three-weekly schedule: 6 mg/kg) should be administered as soon as possible. Do not wait until the next planned cycle. Subsequent HERCESSITMmaintenance doses should be administered 7 days or 21 days later according to the weekly or three-weekly schedules, respectively.

If the patient has missed a dose of HERCESSITMby more than one week, a re-loading dose of HERCESSITMshould be administered over approximately 90 minutes (weekly schedule: 4 mg/kg; three- weekly schedule: 8 mg/kg) as soon as possible. Subsequent HERCESSITMmaintenance doses (weekly schedule: 2 mg/kg; three-weekly schedule 6 mg/kg) should be administered 7 days or 21 days later according to the weekly or three-weekly schedules, respectively.

2.5 Dosage Modifications for Adverse Reactions

Infusion Reactions
[See Boxed Warning, Warnings and Precautions (5.2)]
• Decrease the rate of infusion for mild or moderate infusion reactions
• Interrupt the infusion in patients with dyspnea or clinically significant hypotension
• Discontinue HERCESSITMfor severe or life-threatening infusion reactions.

Cardiomyopathy
[See Boxed Warning, Warnings and Precautions (5.1)]
Assess left ventricular ejection fraction (LVEF) prior to initiation of HERCESSITMand at regular intervals during treatment. Withhold HERCESSITMdosing for at least 4 weeks for either of the following:
• ≥ 16% absolute decrease in LVEF from pre-treatment values
• LVEF below institutional limits of normal and ≥ 10% absolute decrease in LVEF from pretreatment values.

HERCESSITMmay be resumed if, within 4-8 weeks, the LVEF returns to normal limits and the absolute decrease from baseline is ≤ 15%.

Permanently discontinue HERCESSITMfor a persistent (> 8 weeks) LVEF decline or for suspension of HERCESSITMdosing on more than 3 occasions for cardiomyopathy.

2.6 Preparation Instructions

To prevent medication errors, it is important to check the vial labels to ensure that the drug being prepared and administered is HERCESSITM(trastuzumab-strf) and not ado-trastuzumab emtansine or fam-trastuzumab deruxtecan.

420 mg Multiple-dose vial

Reconstitution
Reconstitute each 420 mg vial of HERCESSITMwith 20 mL of Bacteriostatic Water for Injection (BWFI), containing 0.9% to 1.1% benzyl alcohol as a preservative (not supplied) to yield a multiple-dose solution containing 21 mg/mL trastuzumab-strf that delivers 20 mL (420 mg trastuzumab-strf). In patients with known hypersensitivity to benzyl alcohol, reconstitute with 20 mL of Sterile Water for Injection (SWFI) without preservative to yield a one-time use solution.
Use appropriate aseptic technique when performing the following reconstitution steps:
• Using a sterile syringe, slowly inject the 20 mL of diluent (not supplied) into the vial containing the lyophilized powder of HERCESSITM, which has a cake-like appearance. The stream of diluent should be directed into the cake. The reconstituted vial yields a solution for multiple-dose use, containing 21 mg/mL trastuzumab-strf.
• Swirl the vial gently to aid reconstitution. DO NOT SHAKE.
• Slight foaming of the product may be present upon reconstitution. Allow the vial to stand undisturbed for approximately 5 minutes.
• Parenteral drug products should be inspected visually for particulate matter and discoloration prior to administration, whenever solution and container permit. Inspect visually for particulates and discoloration. The solution should be free of visible particulates, clear to slightly opalescent and colorless to pale yellow.
• Store reconstituted HERCESSITMin the refrigerator at 2°C to 8°C (36°F to 46°F) ; discard unused HERCESSITMafter 28 days. If HERCESSITMis reconstituted with SWFI without preservative, use immediately and discard any unused portion. Do not freeze.

Dilution
• Determine the dose (mg) of HERCESSITM [see Dosage and Administration (2.2)].Calculate the volume of the 21 mg/mL reconstituted HERCESSITMsolution needed, withdraw this amount from the vial and add it to an infusion bag containing 250 mL of 0.9% Sodium Chloride Injection. DO NOT USE DEXTROSE (5%) SOLUTION.
• Gently invert the bag to mix the solution.
• The solution of HERCESSITMfor infusion diluted in polyvinylchloride or polypropylene bags containing 0.9% Sodium Chloride Injection, should be stored at 2°C to 8°C (36°F to 46°F) for no more than 24 hours prior to use. This storage time is additional to the time allowed for the reconstituted vials. Do not freeze.

150 mg Single-dose vial

Reconstitution
Reconstitute each 150 mg vial of HERCESSITMwith 7.4 mL of Sterile Water for Injection (SWFI) (not supplied) to yield a single-dose solution containing 21 mg/mL trastuzumab-strf that delivers 7.15 mL (150 mg trastuzumab-strf).

Use appropriate aseptic technique when performing the following reconstitution steps:
• Using a sterile syringe, slowly inject 7.4 mL of SWFI (not supplied) into the vial containing the lyophilized powder of HERCESSITM, which has a cake-like appearance. The stream of diluent should be directed into the cake. The reconstituted vial yields a solution containing 21 mg/mL trastuzumab-strf.
• Swirl the vial gently to aid reconstitution. DO NOT SHAKE.
• Slight foaming of the product may be present upon reconstitution. Allow the vial to stand undisturbed for approximately 5 minutes.
• Parenteral drug products should be inspected visually for particulate matter and discoloration prior to administration, whenever solution and container permit. Inspect visually for particulates and discoloration. The solution should be free of visible particulates, clear to slightly opalescent and colorless to pale yellow.
• Use the HERCESSITMsolution immediately following reconstitution with SWFI, as it contains no preservative and is intended for one-time use only. If not used immediately, store the reconstituted HERCESSITMsolution for up to 24 hours at 2⁰C to 8⁰C (36⁰F to 46⁰F) ; discard any unused HERCESSITMafter 24 hours. Do not freeze.Protect the reconstituted solution from light.

Dilution
• Determine the dose (mg) of HERCESSITM [see Dosage and Administration (2.3)].
• Calculate the volume of the 21 mg/mL reconstituted HERCESSITMsolution needed.
• Withdraw this amount from the vial using a sterile needle and syringe and add it to an infusion bag containing 250 mL of 0.9% Sodium Chloride Injection. DO NOT USE DEXTROSE (5%) SOLUTION.
• Gently invert the bag to mix the solution. Do not shake.
• The solution of HERCESSITMfor infusion diluted in polyvinylchloride or polypropylene bags containing 0.9% Sodium Chloride Injection, should be stored at 2°C to 8°C (36°F to 46°F) for no more than 24 hours or at 30°C to 35°C (86°F to 95°F) for no more than 6 hours prior to use. Discard any unused HERCESSITMafter 24 hours when stored at 2°C to 8°C (36°F to 46°F) or after 6 hours when stored at 30°C to 35°C (86°F to 95°F). This storage time is additional to the time allowed for the reconstituted vials. Do not freeze.

3 DOSAGE FORMS AND STRENGTHS

• For injection: 150 mg white to pale yellow lyophilized powder with a cake-like appearance in a single-dose vial.
• For injection: 420 mg white to pale yellow lyophilized powder with a cake-like appearance in a multiple-dose vial.

4 CONTRAINDICATIONS

None.

5 WARNINGS AND PRECAUTIONS

5.1 Cardiomyopathy

Trastuzumab products can cause left ventricular cardiac dysfunction, arrhythmias, hypertension, disabling cardiac failure, cardiomyopathy, and cardiac death [see Boxed Warning: Cardiomyopathy]. Trastuzumab products can also cause asymptomatic decline in left ventricular ejection fraction (LVEF).
There is a 4-6 fold increase in the incidence of symptomatic myocardial dysfunction among patients receiving trastuzumab products as a single agent or in combination therapy compared with those not receiving trastuzumab products. The highest absolute incidence occurs when trastuzumab product is administered with an anthracycline. Withhold HERCESSITMfor ≥16% absolute decrease in LVEF from pre-treatment values or an LVEF value below institutional limits of normal and ≥ 10% absolute decrease in LVEF from pretreatment values [see Dosage and Administration (2.5)]. The safety of continuation or resumption of trastuzumab products in patients with trastuzumab product-induced left ventricular cardiac dysfunction has not been studied. Patients who receive anthracycline after stopping Hercessi may also be at increased risk of cardiac dysfunction [see Drug Interactions (7) and Clinical Pharmacology (12.3)] . Cardiac Monitoring Conduct thorough cardiac assessment, including history, physical examination, and determination of LVEF by echocardiogram or MUGA scan. The following schedule is recommended:
• Baseline LVEF measurement immediately prior to initiation of HERCESSITM
• LVEF measurements every 3 months during and upon completion of HERCESSITM
• Repeat LVEF measurement at 4 week intervals if HERCESSITMis withheld for significant left ventricular cardiac dysfunction [see Dosage and Administration (2.5)]
• LVEF measurements every 6 months for at least 2 years following completion of HERCESSITMas a component of adjuvant therapy.In NSABP B31, 15% (158/1031) of patients discontinued trastuzumab due to clinical evidence of myocardial dysfunction or significant decline in LVEF after a median follow-up duration of 8.7 years in the AC-TH (anthracycline, cyclophosphamide, paclitaxel, and trastuzumab) arm. In HERA (one-year trastuzumab treatment), the number of patients who discontinued trastuzumab due to cardiac toxicity at 12.6 months median duration of follow-up was 2.6% (44/1678). In BCIRG006, a total of 2.9% (31/1056) of patients in the TCH (docetaxel, carboplatin, trastuzumab) arm (1.5% during the chemotherapy phase and 1.4% during the monotherapy phase) and 5.7% (61/1068) of patients in the AC TH arm (1.5% during the chemotherapy phase and 4.2% during the monotherapy phase) discontinued trastuzumab due to cardiac toxicity.Among 64 patients receiving adjuvant chemotherapy (NSABP B31 and NCCTG N9831) who developed congestive heart failure, one patient died of cardiomyopathy, one patient died suddenly without documented etiology, and 33 patients were receiving cardiac medication at last follow-up. Approximately 24% of the surviving patients had recovery to a normal LVEF (defined as ≥ 50%) and no symptoms on continuing medical management at the time of last follow-up. Incidence of congestive heart failure (CHF) is presented in Table 1. The safety of continuation or resumption of trastuzumab products in patients with trastuzumab product-induced left ventricular cardiac dysfunction has not been studied.

Table 1 Incidence of Congestive Heart Failure in Adjuvant Breast Cancer Studies
 |  | Incidence of Congestive Heart Failure; % (n)
Study | Regimen | Trastuzumab | Control
NSABP B31 & NCCTG N9831a | ACb→ Paclitaxel+Trastuzumab | 3.2% (64/2000)c | 1.3% (21/1655)
HERAd | Chemo → Trastuzumab | 2% (30/1678) | 0.3% (5/1708)
BCIRG006 | ACb→ Docetaxel+Trastuzumab | 2% (20/1068) | 0.3% (3/1050)
BCIRG006 | Docetaxel+Carbo+Trastuzumab | 0.4% (4/1056) | 0.3% (3/1050)

a Median follow-up duration for NSABP B31 and NCCTG N9831 combined was 8.3 years in the AC→paclitaxel+trastuzumab arm.
bAnthracycline (doxorubicin) and cyclophosphamide.
cIncludes 1 patient with fatal cardiomyopathy and 1 patient with sudden death without documented etiology.
dIncludes NYHA II-IV and cardiac death at 12.6 months median duration of follow-up in the one-year trastuzumab arm.In HERA (one-year trastuzumab treatment), at a median follow-up duration of 8 years, the incidence of severe CHF (NYHA III & IV) was 0.8%, and the rate of mild symptomatic and asymptomatic left ventricular dysfunction was 4.6%..

Table 2: Incidence of Cardiac Dysfunctionain Metastatic Breast Cancer Studies
 |  | Incidence
 |  | NYHA I-IV |  | NYHA III-IV
Study | Event | Trastuzumab | Control | Trastuzumab | Control
H0648g (AC)b | Cardiac Dysfunction | 28% | 7% | 19% | 3%
H0648g (paclitaxel) | Cardiac Dysfunction | 11% | 1% | 4% | 1%
H0649g | Cardiac Dysfunctionc | 7% | N/A | 5% | N/A

aCongestive heart failure or significant asymptomatic decrease in LVEF.
bAnthracycline (doxorubicin or epirubicin) and cyclophosphamide.
cIncludes 1 patient with fatal cardiomyopathy. In BCIRG006, the incidence of NCI-CTC Grade 3/4 cardiac ischemia/infarction was higher in the trastuzumab containing regimens (AC-TH: 0.3% (3/1068) and TCH: 0.2% (2/1056)) as compared to none in AC-T

5.2 Infusion Reactions

Infusion reactions consist of a symptom complex characterized by fever and chills, and on occasion included nausea, vomiting, pain (in some cases at tumor sites), headache, dizziness, dyspnea, hypotension, rash, and asthenia [see Adverse Reactions (6.1)].

In post-marketing reports, serious and fatal infusion reactions have been reported. Severe reactions, which include bronchospasm, anaphylaxis, angioedema, hypoxia, and severe hypotension were usually reported during or immediately following the initial infusion. However, the onset and clinical course were variable, including progressive worsening, initial improvement followed by clinical deterioration, or delayed post-infusion events with rapid clinical deterioration. For fatal events, death occurred within hours to days following a serious infusion reaction.

Interrupt HERCESSITMinfusion in all patients experiencing dyspnea, clinically significant hypotension, and intervention of medical therapy administered (which may include epinephrine, corticosteroids, diphenhydramine, bronchodilators, and oxygen). Patients should be evaluated and carefully monitored until complete resolution of signs and symptoms. Permanent discontinuation should be strongly considered in all patients with severe infusion reactions.

There are no data regarding the most appropriate method of identification of patients who may safely be retreated with trastuzumab products after experiencing a severe infusion reaction. Prior to resumption of trastuzumab infusion, the majority of patients who experienced a severe infusion reaction were pre-medicated with antihistamines and/or corticosteroids. While some patients tolerated Trastuzumab infusions, others had recurrent severe infusion reactions despite pre-medications.

5.3 Embryo-Fetal Toxicity

Trastuzumab products can cause fetal harm when administered to a pregnant woman. In post-marketing reports, use of trastuzumab during pregnancy resulted in cases of oligohydramnios and oligohydramnios sequence manifesting as pulmonary hypoplasia, skeletal abnormalities, and neonatal death.

Verify the pregnancy status of females of reproductive potential prior to the initiation of HERCESSITM. Advise pregnant women and females of reproductive potential that exposure to HERCESSITMduring pregnancy or within 7 months prior to conception can result in fetal harm. Advise females of reproductive potential to use effective contraception during treatment and for 7 months following the last dose of HERCESSITM [see Use in Specific Populations (8.1,8.3)and Clinical Pharmacology (12.3)].

5.4 Pulmonary Toxicity

Trastuzumab product use can result in serious and fatal pulmonary toxicity. Pulmonary toxicity includes dyspnea, interstitial pneumonitis, pulmonary infiltrates, pleural effusions, non-cardiogenic pulmonary edema, pulmonary insufficiency and hypoxia, acute respiratory distress syndrome, and pulmonary fibrosis. Such events can occur as sequelae of infusion reactions [see Warnings and Precautions (5.2)].Patients with symptomatic intrinsic lung disease or with extensive tumor involvement of the lungs, resulting in dyspnea at rest, appear to have more severe toxicity.

5.5 Exacerbation of Chemotherapy-Induced Neutropenia

In randomized, controlled clinical trials, the per-patient incidences of NCI-CTC Grade 3-4 neutropenia and of febrile neutropenia were higher in patients receiving trastuzumab in combination with myelosuppressive chemotherapy as compared to those who received chemotherapy alone. The incidence of septic death was similar among patients who received trastuzumab and those who did not [see Adverse Reactions (6.1)].

6 ADVERSE REACTIONS

The following adverse reactions are discussed in greater detail in other sections of the label:

- Cardiomyopathy [see Warnings and Precautions (5.1)]
- Infusion Reactions [see Warnings and Precautions (5.2)]
- Embryo-Fetal Toxicity [see Warnings and Precautions (5.3)]
- Pulmonary Toxicity [see Warnings and Precautions (5.4)]
- Exacerbation of Chemotherapy-Induced Neutropenia [see Warnings and Precautions (5.5)]

6.1 Clinical Trials Experience

Because clinical trials are conducted under widely varying conditions, adverse reaction rates observed in the clinical trials of a drug cannot be directly compared to rates in the clinical trials of another drug and may not reflect the rates observed in practice.

The most common adverse reactions in patients receiving trastuzumab products in the adjuvant and metastatic breast cancer setting are fever, nausea, vomiting, infusion reactions, diarrhea, infections, increased cough, headache, fatigue, dyspnea, rash, neutropenia, anemia, and myalgia. Adverse reactions requiring interruption or discontinuation of trastuzumab product treatment include CHF, significant decline in left ventricular cardiac function, severe infusion reactions, and pulmonary toxicity [see Dosage and Administration (2.5)].

In the metastatic gastric cancer setting, the most common adverse reactions (≥ 10%) that were increased (≥ 5% difference) in the trastuzumab arm as compared to the chemotherapy alone arm were neutropenia, diarrhea, fatigue, anemia, stomatitis, weight loss, upper respiratory tract infections, fever, thrombocytopenia, mucosal inflammation, nasopharyngitis, and dysgeusia.

The most common adverse reactions which resulted in discontinuation of treatment on the trastuzumab-containing arm in the absence of disease progression were infection, diarrhea, and febrile neutropenia.

Adjuvant Breast Cancer
The information below reflects exposure to one-year trastuzumab therapy across three randomized, open-label studies, Studies 1, 2, and 3, with (n = 3678) or without (n = 3363) trastuzumab in the adjuvant treatment of breast cancer.

HERA
Table 3 reflects exposure to trastuzumab in 1678 patients in HERA; the median treatment duration was 51 weeks and median number of infusions was 18 [see Clinical Studies (14.1)].

Table 3: Adverse Reactions (≥1%) in HERA (All Grades)a
 | Trastuzumab | Observation
Adverse Reactions | (n = 1678) % | (n = 1708) %
Nervous System
Headache | 10 | 3
Paresthesia | 2 | 0.6
Musculoskeletal
Arthralgia | 8 | 6
Back pain | 5 | 3
Myalgia | 4 | 1
Bone pain | 3 | 2
Muscle spasm | 3 | 0.2
Infections
Nasopharyngitis | 8 | 3
Urinary tract infection | 3 | 0.8
Gastrointestinal
Diarrhea | 7 | 1
Nausea | 6 | 1
Vomiting | 3.5 | 0.6
Constipation | 2 | 1
Dyspepsia | 2 | 0.5
Upper abdominal pain | 2 | 1
General
Pyrexia | 6 | 0.4
Peripheral edema | 5 | 2
Chills | 5 | 0
Asthenia | 4.5 | 2
Influenza-like illness | 2 | 0.2
Respiratory Thoracic Mediastinal
Cough | 5 | 2
Influenza | 4 | 0.5
Dyspnea | 3 | 2
URI | 3 | 1
Rhinitis | 2 | 0.4
Pharyngolaryngeal pain | 2 | 0.5
Sinusitis | 2 | 0.3
Epistaxis | 2 | 0.06
Cardiac
Hypertension | 4 | 2
Dizziness | 4 | 2
Ejection fraction decreased | 3.5 | 0.6
Palpitations | 3 | 0.7
Cardiac arrhythmiasb | 3 | 1
Cardiac failure (congestive) | 2 | 0.3
Skin & Subcutaneous Tissue
Rash | 4 | 0.6
Nail disorders | 2 | 0
Pruritus | 2 | 0.6

a The incidence of Grade 3 or higher adverse reactions was <1% in both arms for each listed term.
b Higher level grouping term.

Clinically relevant adverse reactions in < 1% of patients who received trastuzumab in HERA included hypersensitivity (0.6%), cardiac failure (0.5%), cardiac disorder (0.3%), interstitial pneumonitis (0.2%), pulmonary hypertension (0.2%), ventricular disorder (0.2%), autoimmune thyroiditis (0.3%), and sudden death (0.06%).

Adjuvant Treatment of Breast Cancer with Trastuzumab Beyond One Year
Extending adjuvant treatment beyond one year is not recommended [see Dosage and Administration (2.2)]. In HERA, a comparison of trastuzumab administered once every 3 weeks for two years versus one year was performed. The rate of asymptomatic cardiac dysfunction was increased in the 2-year trastuzumab compared to the 1-year trastuzumab treatment arm (8.1% versus 4.6%, respectively). More patients experienced at least one adverse reaction of Grade 3 or higher in the 2-year trastuzumab treatment arm (20.4%) compared with the one-year trastuzumab treatment arm (16.3%).

NSABP B31 and NCCTG N9831
The safety data from NSABP B31 and NCCTG N9831 were obtained from 3655 patients, of whom 2000 received trastuzumab; the median treatment duration was 51 weeks [see Clinical Studies (14.1)].

In NSABP B31, only Grade 3−5 adverse events, treatment-related Grade 2 events, and Grade 2−5 dyspnea were collected during and for up to 3 months following protocol-specified treatment. The following non-cardiac adverse reactions of Grade 2−5 occurred at an incidence of at least 2% greater among patients receiving trastuzumab plus chemotherapy as compared to chemotherapy alone: fatigue (29.5% vs. 22.4%), infection (24.0% vs. 12.8%), hot flashes (17.1% vs. 15%), anemia (12.3% vs. 6.7%), dyspnea (11.8% vs. 4.6%), rash/desquamation (10.9% vs. 7.6%), leukopenia (10.5% vs. 8.4%), neutropenia (6.4% vs. 4.3%), headache (6.2% vs. 3.8%), pain (5.5% vs. 3%), edema (4.7% vs. 2.7%), and insomnia (4.3% vs. 1.5%). The majority of these events were Grade 2 in severity.

In NCCTG N9831, data collection was limited to the following investigator-attributed treatment-related adverse reactions: NCI-CTC Grade 4 and 5 hematologic toxicities, Grade 3−5 non-hematologic toxicities, selected Grade 2−5 toxicities associated with taxanes (myalgia, arthralgias, nail changes, motor neuropathy, and sensory neuropathy) and Grade 1−5 cardiac toxicities occurring during chemotherapy and/or trastuzumab treatment. The following non-cardiac adverse reactions of Grade 2−5 occurred at an incidence of at least 2% greater among patients receiving trastuzumab plus chemotherapy as compared to chemotherapy alone: arthralgia (12.2% vs. 9.1%), nail changes (11.5% vs. 6.8%), dyspnea (2.4% vs. 0.2%), and diarrhea (2.2% vs. 0%). The majority of these events were Grade 2 in severity.

BCIRG006
Safety data from BCIRG006 reflect exposure to trastuzumab as part of an adjuvant treatment regimen from 2124 patients receiving at least one dose of study treatment [AC-TH: n = 1068; TCH: n=1056]. The overall median treatment duration was 54 weeks in both the AC-TH and TCH arms. The median number of infusions was 26 in the AC-TH arm and 30 in the TCH arm, including weekly infusions during the chemotherapy phase and once every three week dosing in the monotherapy period [see Clinical Studies (14.1)].In BCIRG006, the toxicity profile was similar to that reported in Studies NSABP B31, NCCTG N9831, and HERA with the exception of a lower incidence of CHF in the TCH arm.

Metastatic Breast Cancer Studies
The safety of trastuzumab was evaluated in one randomized, open-label study (H0648g) of chemotherapy with (n = 235) or without (n = 234) intravenous trastuzumab in patients with metastatic breast cancer and in one single-arm study (H0649g); in patients with metastatic breast cancer (n=222) [see Clinical Studies (14.1)].Patients received 4 mg/kg initial dose of trastuzumab followed by 2 mg/kg weekly. In H0648g, 58% of patients received trastuzumab for ≥ 6 months and 9% received trastuzumab ≥ 12 months, respectively. In H0649g, 31% of patients received trastuzumab for ≥ 6 months and 16% received trastuzumab for ≥ 12 months, respectively.

Table 4 shows the adverse reactions (≥ 5%) in patients from H0648g and H0649g.

Table 4 : Adverse Reactionsa (5%) in the Trastuzumab Arms in H0648g and H0649g
 | Trastuzumaba n = 352 % | Trastuzumab + Paclitaxel n = 91 % | Paclitaxel n = 95 % | Trastuzumab + ACb n = 143 % | ACb n = 135 %
General
Pain | 47 | 61 | 62 | 57 | 42
Asthenia | 42 | 62 | 57 | 54 | 55
Fever | 36 | 49 | 23 | 56 | 34
Chills | 32 | 41 | 4 | 35 | 11
Headache | 26 | 36 | 28 | 44 | 31
Abdominal pain | 22 | 34 | 22 | 23 | 18
Back pain | 22 | 34 | 30 | 27 | 15
Infection | 20 | 47 | 27 | 47 | 31
Flu syndrome | 10 | 12 | 5 | 12 | 6
Accidental injury | 6 | 13 | 3 | 9 | 4
Allergic reaction | 3 | 8 | 2 | 4 | 2
Gastrointestinal
Nausea | 33 | 51 | 9 | 76 | 77
Diarrhea | 25 | 45 | 29 | 45 | 26
Vomiting | 23 | 37 | 28 | 53 | 49
Anorexia | 14 | 24 | 16 | 31 | 26
Nausea and vomiting | 8 | 14 | 11 | 18 | 9
Respiratory
Cough increased | 26 | 41 | 22 | 43 | 29
Dyspnea | 22 | 27 | 26 | 42 | 25
Rhinitis | 14 | 22 | 5 | 22 | 16
Pharyngitis | 12 | 22 | 14 | 30 | 18
Sinusitis | 9 | 21 | 7 | 13 | 6
Skin
Rash | 18 | 38 | 18 | 27 | 17
Herpes simplex | 2 | 12 | 3 | 7 | 9
Acne | 2 | 11 | 3 | 3 | <1
Nervous
Insomnia | 14 | 25 | 13 | 29 | 15
Dizziness | 13 | 22 | 24 | 24 | 18
Paresthesia | 9 | 48 | 39 | 17 | 11
Depression | 6 | 12 | 13 | 20 | 12
Peripheral neuritis | 2 | 23 | 16 | 2 | 2
Neuropathy | 1 | 13 | 5 | 4 | 4
Metabolic
Peripheral edema | 10 | 22 | 20 | 20 | 17
Edema | 8 | 10 | 8 | 11 | 5
Cardiovascular
Congestive heart failure | 7 | 11 | 1 | 28 | 7
Tachycardia | 5 | 12 | 4 | 10 | 5
Musculoskeletal
Bone pain | 7 | 24 | 18 | 7 | 7
Arthralgia | 6 | 37 | 21 | 8 | 9
Urogenital
Urinary tract infection | 5 | 18 | 14 | 13 | 7
Blood & Lymphatic
Anemia | 4 | 14 | 9 | 36 | 36
Leukopenia | 3 | 24 | 17 | 52 | 34

aData for trastuzumab single agent were from 4 studies, including 213 patients from H0649g.
bAnthracycline (doxorubicin or epirubicin) and cyclophosphamide.

Metastatic Gastric Cancer

The safety of trastuzumab was evaluated in patients with previously untreated for metastatic gastric or gastroesophageal junction adenocarcinoma in an open label, multi-center trial (ToGA) [see Clinical Studies (14.3)]. Patients were randomized (1:1) to receive trastuzumab in combination with cisplatin and a fluoropyrimidine (FC+H) (n=294) or chemotherapy alone (FC) (n=290). Patients in the trastuzumab plus chemotherapy arm received trastuzumab 8 mg/kg administered on Day 1 (prior to chemotherapy) followed by 6 mg/kg every 21 days until disease progression. Cisplatin was administered at 80 mg/m2 on Day 1 and the fluoropyrimidine was administered as either capecitabine 1000 mg/m2 orally twice a day on Days 1–14 or 5-fluorouracil 800 mg/m2/day as a continuous intravenous infusion Days 1 through 5. Chemotherapy was administered for six 21-day cycles. Median duration of trastuzumab treatment was 21 weeks and the median number of trastuzumab infusions administered was eight.

Table 5: Adverse Reactions (All Grades ≥ 5% or Grade 3-4 ≥ 1% between Arms) in ToGA
Adverse Reactions | Trastuzumab + FC (N = 294) % |  | FC (N = 290) %
 | All Grades | Grades 3/4 | All Grades | Grades 3/4
Investigations
Neutropenia | 78 | 34 | 73 | 29
Hypokalemia | 28 | 10 | 24 | 6
Anemia | 28 | 12 | 21 | 10
Thrombocytopenia | 16 | 5 | 11 | 3
Blood and Lymphatic System Disorders
Febrile Neutropenia | — | 5 | — | 3
Gastrointestinal Disorders
Diarrhea | 37 | 9 | 28 | 4
Stomatitis | 24 | 1 | 15 | 2
Dysphagia | 6 | 2 | 3 | <1
General
Fatigue | 35 | 4 | 28 | 2
Fever | 18 | 1 | 12 | 0
Mucosal Inflammation | 13 | 2 | 6 | 1
Chills | 8 | <1 | 0 | 0
Metabolism and Nutrition Disorders
Weight Decrease | 23 | 2 | 14 | 2
Infections and Infestations
Upper Respiratory Tract Infections | 19 | 0 | 10 | 0
Nasopharyngitis | 13 | 0 | 6 | 0
Renal and Urinary Disorders
Renal Failure and Impairment | 18 | 3 | 15 | 2
Nervous System Disorders
Dysgeusia | 10 | 0 | 5 | 0

The following subsections provide additional detail regarding adverse reactions observed in clinical trials of adjuvant breast cancer, metastatic breast cancer, metastatic gastric cancer, or post-marketing experience.

Cardiomyopathy

Serial measurement of cardiac function (LVEF) was obtained in clinical trials in the adjuvant treatment of breast cancer. In HERA, the median duration of follow-up was 12.6 months (12.4 months in the observation arm; 12.6 months in the 1-year trastuzumab arm); and in NSABP B31 and NCCTG N9831, 7.9 years in the AC-T arm, 8.3 years in the AC-TH arm. Following initiation of trastuzumab therapy, the incidence of new-onset dose-limiting myocardial dysfunction was higher among patients receiving trastuzumab and paclitaxel as compared to those receiving paclitaxel alone in NSABP B31 and NCCTG N9831, and in patients receiving one-year trastuzumab monotherapy compared to observation in HERA (see Table 6, Figures 1 and 2). The incidence of new-onset cardiac dysfunction, as measured by LVEF, remained similar when compared to the analysis performed at a median follow-up of 2.0 years in the AC-TH arm. This analysis showed evidence of reversibility of left ventricular dysfunction, with 64.5% of patients who experienced symptomatic CHF in the AC-TH group being asymptomatic at latest follow-up, and 90.3% having full or partial LVEF recovery.

Table 6: Myocardial Dysfunction (by LVEF) in Studies 1, 2, 3 and 4a
Study and Arm | LVEF < 50% and Absolute Decrease from Baseline |  |  | LVEF Decrease
 | LVEF < 50% | ≥ 10% decrease | ≥ 16% decrease | < 20% and ≥ 10% | ≥ 20%
Studies 1 & 2b,c
AC→TH (n = 1856) | 23.1% (428) | 18.5% (344) | 11.2% (208) | 37.9% (703) | 8.9% (166)
AC→T (n = 1170) | 11.7% (137) | 7.0% (82) | 3.0% (35) | 22.1% (259) | 3.4% (40)
HERAd
Trastuzumab (n = 1678) | 8.6% (144) | 7.0% (118) | 3.8% (64) | 22.4% (376) | 3.5% (59)
Observation (n = 1708) | 2.7% (46) | 2.0% (35) | 1.2% (20) | 11.9% (204) | 1.2% (21)
BCIRG006e
TCH (n = 1056) | 8.5% (90) | 5.9% (62) | 3.3% (35) | 34.5% (364) | 6.3% (67)
AC→TH (n = 1068) | 17% (182) | 13.3% (142) | 9.8% (105) | 44.3% (473) | 13.2% (141)
AC→T (n = 1050) | 9.5% (100) | 6.6% (69) | 3.3% (35) | 34% (357) | 5.5% (58)

aFor Studies 1, 2 and 3, events are counted from the beginning of trastuzumab treatment. For Study BCIRG006, events are counted from the date of randomization.
b NSABP B31 and NCCTG N9831: doxorubicin and cyclophosphamide followed by paclitaxel (AC→T) or paclitaxel plus trastuzumab (AC→TH).
cMedian duration of follow-up for NSABP B31 and NCCTG N9831 combined was 8.3 years in the AC→TH arm.
dMedian follow-up duration of 12.6 months in the one-year trastuzumab treatment arm.
e BCIRG006 regimens: doxorubicin and cyclophosphamide followed by docetaxel (AC→T) or docetaxel plus trastuzumab (AC→TH); docetaxel and carboplatin plus trastuzumab (TCH).

Figure 1
NSABP B31 and NCCTG N9831: Cumulative Incidence of Time to First LVEF Decline of ≥ 10 Percentage Points from Baseline and to Below 50% with Death as a Competing Risk Event

Time 0 is initiation of paclitaxel or trastuzumab + paclitaxel therapy.

Figure 2
HERA: Cumulative Incidence of Time to First LVEF Decline of ≥ 10 Percentage Points from Baseline and to Below 50% with Death as a Competing Risk Event

Time 0 is the date of randomization.

Figure 3
BCIRG006: Cumulative Incidence of Time to First LVEF Decline of ≥10 Percentage Points from Baseline and to Below 50% with Death as a Competing Risk Eventt

Time 0 is the date of randomization.

The incidence of congestive heart failure among patients in the metastatic breast cancer trials was classified for severity using the New York Heart Association classification system (I-IV, where IV is the most severe level of cardiac failure) (see Table 2). In the metastatic breast cancer trials, the probability of cardiac dysfunction was highest in patients who received trastuzumab concurrently with anthracyclines.

In ToGA, 5% of patients in the trastuzumab plus chemotherapy arm compared to 1.1% of patients in the chemotherapy alone arm had LVEF value below 50% with a ≥ 10% absolute decrease in LVEF from pretreatment values.

Infusion Reactions
During the first infusion with trastuzumab, the symptoms most commonly reported were chills and fever, occurring in approximately 40% of patients in clinical trials. Symptoms were treated with acetaminophen, diphenhydramine, and meperidine (with or without reduction in the rate of trastuzumab infusion); permanent discontinuation of trastuzumab for infusion reactions was required in < 1% of patients. Other signs and/or symptoms may include nausea, vomiting, pain (in some cases at tumor sites), rigors, headache, dizziness, dyspnea, hypotension, elevated blood pressure, rash, and asthenia. Infusion reactions occurred in 21% and 35% of patients, and were severe in 1.4% and 9% of patients, on second or subsequent trastuzumab infusions administered as monotherapy or in combination with chemotherapy, respectively. In the post-marketing setting, severe infusion reactions, including hypersensitivity, anaphylaxis, and angioedema have been reported.

Anemia
In randomized controlled clinical trials, the overall incidence of anemia (30% vs. 21% [H0648g]), of selected NCI-CTC Grade 2–5 anemia (12.3% vs. 6.7% [NSABP B31]), and of anemia requiring transfusions (0.1% vs. 0 patients [NCCTG N9831]) were increased in patients receiving trastuzumab and chemotherapy compared with those receiving chemotherapy alone. Following the administration of trastuzumab as a single agent (H0649g), the incidence of NCI-CTC Grade 3 anemia was < 1%. In ToGA (metastatic gastric cancer), on the trastuzumab containing arm as compared to the chemotherapy alone arm, the overall incidence of anemia was 28% compared to 21% and of NCI CTC Grade 3/4 anemia was 12.2% compared to 10.3%.

Neutropenia
In randomized controlled clinical trials in the adjuvant setting, the incidence of selected NCI-CTC Grade 45 neutropenia (1.7% vs. 0.8% [NCCTG N9831]) and of selected Grade 25 neutropenia (6.4% vs. 4.3% [NSABP B31]) were increased in patients receiving trastuzumab and chemotherapy compared with those receiving chemotherapy alone. In a randomized, controlled trial in patients with metastatic breast cancer, the incidences of NCI-CTC Grade 3/4 neutropenia (32% vs. 22%) and of febrile neutropenia (23% vs. 17%) were also increased in patients randomized to trastuzumab in combination with myelosuppressive chemotherapy as compared to chemotherapy alone. In ToGA (metastatic gastric cancer) on the trastuzumab containing arm as compared to the chemotherapy alone arm, the incidence of NCI-CTC Grade 3/4 neutropenia was 36.8% compared to 28.9%; febrile neutropenia 5.1% compared to 2.8%.

Infection
The overall incidences of infection (46% vs. 30% [H0648g]), of selected NCI-CTC Grade 25 infection/febrile neutropenia (24.3% vs. 13.4% [NSABP B31]) and of selected Grade 35 infection/febrile neutropenia (2.9% vs. 1.4% [NCCTG N9831]) were higher in patients receiving trastuzumab and chemotherapy compared with those receiving chemotherapy alone. The most common site of infections in the adjuvant setting involved the upper respiratory tract, skin, and urinary tract.

In BCIRG006, the overall incidence of infection was higher with the addition of trastuzumab to AC-T but not to TCH [44% (AC-TH), 37% (TCH), 38% (AC-T)]. The incidences of NCI-CTC Grade 3-4 infection were similar [25% (AC-TH), 21% (TCH), 23% (AC-T)] across the three arms.

In a randomized, controlled trial in treatment of metastatic breast cancer, the reported incidence of febrile neutropenia was higher (23% vs. 17%) in patients receiving trastuzumab in combination with myelosuppressive chemotherapy as compared to chemotherapy alone.

Pulmonary Toxicity

Adjuvant Breast Cancer
Among women receiving adjuvant therapy for breast cancer, the incidence of selected NCI-CTC Grade 2-5 pulmonary toxicity (14.3% vs. 5.4% [NSABP B31]) and of selected NCI-CTC Grade 3-5 pulmonary toxicity and spontaneous reported Grade 2 dyspnea (3.4% vs. 0.9% [NCCTG N9831]) was higher in patients receiving trastuzumab and chemotherapy compared with chemotherapy alone. The most common pulmonary toxicity was dyspnea (NCI-CTC Grade 2-5: 11.8% vs. 4.6% [NSABP B31]; NCI-CTC Grade 2-5: 2.4% vs. 0.2% [NCCTG N9831]).

Pneumonitis/pulmonary infiltrates occurred in 0.7% of patients receiving trastuzumab compared with 0.3% of those receiving chemotherapy alone. Fatal respiratory failure occurred in 3 patients receiving trastuzumab, one as a component of multi-organ system failure, as compared to 1 patient receiving chemotherapy alone.

In HERA, there were 4 cases of interstitial pneumonitis in the one-year trastuzumab treatment arm compared to none in the observation arm at a median follow-up duration of 12.6 months.

Metastatic Breast Cancer
Among women receiving trastuzumab for treatment of metastatic breast cancer, the incidence of pulmonary toxicity was also increased. Pulmonary adverse events have been reported in the post- marketing experience as part of the symptom complex of infusion reactions. Pulmonary events include bronchospasm, hypoxia, dyspnea, pulmonary infiltrates, pleural effusions, non-cardiogenic pulmonary edema, and acute respiratory distress syndrome. For a detailed description, see Warnings and Precautions (5.4).

Thrombosis/Embolism
In 4 randomized, controlled clinical trials, the incidence of thrombotic adverse events was higher in patients receiving trastuzumab and chemotherapy compared to chemotherapy alone in three studies (2.6% vs. 1.5% [NSABP B31], 2.5% and 3.7% vs. 2.2% [BCIRG006] and 2.1% vs. 0% [H0648g]).

Diarrhea
Among women receiving adjuvant therapy for breast cancer, the incidence of NCI-CTC Grade 2-5 diarrhea (6.7% vs. 5.4% [NSABP B31]) and of NCI-CTC Grade 3-5 diarrhea (2.2% vs. 0% [NCCTG N9831]), and of Grade 1-4 diarrhea (7% vs. 1% [HERA; one-year trastuzumab treatment at 12.6 months median duration of follow-up]) were higher in patients receiving trastuzumab as compared to controls. In BCIRG006, the incidence of Grade 3-4 diarrhea was higher [5.7% AC-TH, 5.5% TCH vs. 3.0% AC-T] and of Grade 1-4 was higher [51% AC-TH, 63% TCH vs. 43% AC-T] among women receiving trastuzumab. Of patients receiving trastuzumab as a single agent for the treatment of metastatic breast cancer, 25% experienced diarrhea. An increased incidence of diarrhea was observed in patients receiving trastuzumab in combination with chemotherapy for treatment of metastatic breast cancer.

Renal Toxicity
In ToGA (metastatic gastric cancer) on the trastuzumab-containing arm as compared to the chemotherapy alone arm the incidence of renal impairment was 18% compared to 14.5%. Severe (Grade 3/4) renal failure was 2.7% on the trastuzumab-containing arm compared to 1.7% on the chemotherapy only arm. Treatment discontinuation for renal insufficiency/failure was 2% on the trastuzumab-containing arm and 0.3% on the chemotherapy only arm.

In the post-marketing setting, rare cases of nephrotic syndrome with pathologic evidence of glomerulopathy have been reported. The time to onset ranged from 4 months to approximately 18 months from initiation of trastuzumab therapy. Pathologic findings included membranous glomerulonephritis, focal glomerulosclerosis, and fibrillary glomerulonephritis. Complications included volume overload and congestive heart failure.

6.2 Post-Marketing Experience

The following adverse reactions have been identified during post-approval use of trastuzumab products.
Because these reactions are reported voluntarily from a population of uncertain size, it is not always possible to reliably estimate their frequency or establish a causal relationship to drug exposure.
• Infusion reaction [see Warnings and Precautions (5.2)]
• Oligohydramnios or oligohydramnios sequence, including pulmonary hypoplasia, skeletal abnormalities, and neonatal death [see Warnings and Precautions (5.3)]
• Glomerulopathy [see Adverse Reactions (6.1)]
• Immune thrombocytopenia
• Tumor lysis syndrome (TLS): Cases of possible TLS have been reported in patients treated with trastuzumab products. Patients with significant tumor burden (e.g. bulky metastases) may be at a higher risk. Patients could present with hyperuricemia, hyperphosphatemia, and acute renal failure which may represent possible TLS. Providers should consider additional monitoring and/or treatment as clinically indicated.

7 DRUG INTERACTIONS

Anthracyclines
Patients who receive anthracycline after stopping trastuzumab products may be at increased risk of cardiac dysfunction because of trastuzumab products estimated long washout period [see Clinical Pharmacology (12.3)]If possible, avoid anthracycline-based therapy for up to 7 months after stopping trastuzumab products. If anthracyclines are used, closely monitor the patient’s cardiac function.

8 USE IN SPECIFIC POPULATIONS

8.1 Pregnancy

Risk Summary
Trastuzumab products can cause fetal harm when administered to a pregnant woman. In post-marketing reports and published literature, use of trastuzumab during pregnancy resulted in cases of oligohydramnios and of oligohydramnios sequence, manifesting as pulmonary hypoplasia, skeletal abnormalities, and neonatal death [see Data].Apprise the patient of the potential risks to a fetus. There are clinical considerations if a trastuzumab product is used in a pregnant woman or if a patient becomes pregnant within 7 months following the last dose of a trastuzumab product [see Clinical Considerations].

The background risk of major birth defects and miscarriage for the indicated population is unknown. In the U.S. general population, the estimated background risk of major birth defects and miscarriage in clinically recognized pregnancies is 2% to 4% and 15% to 20%, respectively

Clinical Considerations

Fetal/Neonatal Adverse Reactions
Monitor women who received HERCESSITMduring pregnancy or within 7 months prior to conception for oligohydramnios. If oligohydramnios occurs, perform fetal/neonatal testing that is appropriate for gestational age and consistent with community standards of care.

Data

Human Data

In post-marketing reports and published literature, use of trastuzumab during pregnancy resulted in cases of oligohydramnios and of oligohydramnios sequence. Fetal manifestations included pulmonary hypoplasia, skeletal abnormalities, and neonatal death. These case reports described oligohydramnios in pregnant women who received trastuzumab either alone or in combination with chemotherapy. In most reported cases, amniotic fluid index increased after trastuzumab was stopped. In reported cases where trastuzumab therapy was resumed after amniotic index improved, oligohydramnios recurred.

Animal Data

In studies where trastuzumab was administered to pregnant cynomolgus monkeys during the period of organogenesis at doses up to 25 mg/kg given twice weekly (up to 25 times the recommended weekly human dose of 2 mg/kg), trastuzumab crossed the placental barrier during the early (Gestation Days 20 to 50) and late (Gestation Days 120 to 150) phases of gestation. The resulting concentrations of trastuzumab in fetal serum and amniotic fluid were approximately 33% and 25%, respectively, of those present in the maternal serum but were not associated with adverse developmental effects.

8.2 Lactation

Risk Summary

There is no information regarding the presence of trastuzumab products in human milk, the effects on the breastfed infant, or the effects on milk production. Published data suggest human IgG is present in human milk but does not enter the neonatal and infant circulation in substantial amounts.
Trastuzumab was present in the milk of lactating Cynomolgus monkeys but not associated with neonatal toxicity [see Data].Consider the developmental and health benefits of breastfeeding along with the mother’s clinical need for HERCESSITMtreatment and any potential adverse effects on the breastfed child from HERCESSITMor from the underlying maternal condition. This consideration should also take into account the trastuzumab product wash out period of 7 months [see Clinical Pharmacology (12.3)].

Data

In lactating Cynomolgus monkeys, trastuzumab was present in breast milk at about 0.3% of maternal serum concentrations after pre- (beginning Gestation Day 120) and post-partum (through Post-partum Day 28) doses of 25 mg/kg administered twice weekly (25 times the recommended weekly human dose of 2 mg/kg of trastuzumab products). Infant monkeys with detectable serum levels of trastuzumab did not exhibit any adverse effects on growth or development from birth to 1 month of age.

8.3 Females and Males of Reproductive Potential

Pregnancy Testing

Verify the pregnancy status of females of reproductive potential prior to the initiation of HERCESSITM.

Contraception

Females

Trastuzumab products can cause embryo-fetal harm when administered during pregnancy. Advise females of reproductive potential to use effective contraception during treatment with HERCESSITMand for 7 months following the last dose of HERCESSITM [see Use in Specific Populations (8.1) and Clinical Pharmacology (12.3)].

8.4 Pediatric Use

The safety and effectiveness of HERCESSITMin pediatric patients have not been established.

8.5 Geriatric Use

Trastuzumab has been administered to 386 patients who were 65 years of age or over (253 in the adjuvant treatment and 133 in metastatic breast cancer treatment settings). The risk of cardiac dysfunction was increased in geriatric patients as compared to younger patients in both those receiving treatment for metastatic disease in H0648g and H0649g, or adjuvant therapy in NSABP B31 and NCCTG N9831. Limitations in data collection and differences in study design of the 4 studies of trastuzumab in adjuvant treatment of breast cancer preclude a determination of whether the toxicity profile of trastuzumab in older patients is different from younger patients. The reported clinical experience is not adequate to determine whether the efficacy improvements (ORR, TTP, OS, DFS) of trastuzumab treatment in older patients is different from that observed in patients < 65 years of age for metastatic disease and adjuvant treatment.

In ToGA (metastatic gastric cancer), of the 294 patients treated with trastuzumab, 108 (37%) were 65 years of age or older, while 13 (4.4%) were 75 and over. No overall differences in safety or effectiveness were observed.

11 DESCRIPTION

Trastuzumab-strf is a humanized IgG1 kappa monoclonal antibody that selectively binds with high affinity to the extracellular domain of the human epidermal growth factor receptor 2 protein, HER2. Trastuzumab-strf is produced by recombinant DNA technology in a mammalian cell (Chinese Hamster Ovary) culture which may contain the antibiotic puromycin. Puromycin is not detectable in the final product.

HERCESSITM(trastuzumab-strf) for injection is a sterile, white to pale yellow, preservative-free lyophilized powder with a cake-like appearance, for intravenous administration.

Each multiple-dose vial of HERCESSITMdelivers 420 mg trastuzumab-strf, histidine (6.1 mg), L-histidine hydrochloride monohydrate (9.5 mg), polysorbate 20 (1.7 mg), and trehalose (345.44 mg). Reconstitution with 20 mL of the appropriate diluent (BWFI or SWFI) yields a solution containing 21 mg/mL trastuzumab-strf that delivers 20 mL (420 mg trastuzumab-strf), at a pH of approximately 6. If HERCESSITMis reconstituted with SWFI without preservative, the reconstituted solution is considered single-dose.

Each single-dose vial of HERCESSITMdelivers 150 mg trastuzumab-strf, histidine (2.16 mg), L-histidine hydrochloride monohydrate (3.36 mg), polysorbate 20 (0.6 mg), and trehalose (123.229 mg). Reconstitution with 7.4 mL of sterile water for injection (SWFI) yields a solution containing 21 mg/mL trastuzumab-strf that delivers 7.15 mL (150 mg trastuzumab-strf), at a pH of approximately 6.

12 CLINICAL PHARMACOLOGY

12.1 Mechanism of Action

The HER2 (or c-erbB2) proto-oncogene encodes a transmembrane receptor protein of 185 kDa, which is structurally related to the epidermal growth factor receptor. Trastuzumab products have been shown, in both in vitroassays and in animals, to inhibit the proliferation of human tumor cells that overexpress HER2.

Trastuzumab products are mediators of antibody-dependent cellular cytotoxicity (ADCC). In vitro, trastuzumab product-mediated ADCC has been shown to be preferentially exerted on HER2 overexpressing cancer cells compared with cancer cells that do not overexpress HER2.

12.2 Pharmacodynamics

Trastuzumab product exposure-response relationships and the time course of pharmacodynamic responses are not fully characterized.
Cardiac Electrophysiology
The effects of trastuzumab on electrocardiographic (ECG) endpoints, including QTc interval duration, were evaluated in patients with HER2 positive solid tumors. Trastuzumab had no clinically relevant effect on the QTc interval duration and there was no apparent relationship between serum trastuzumab concentrations and change in QTcF interval duration in patients with HER2 positive solid tumors.

12.3 Pharmacokinetics

The pharmacokinetics of trastuzumab was evaluated in a pooled population pharmacokinetic (PK) model analysis of 1,582 subjects with primarily breast cancer and metastatic gastric cancer (MGC) receiving intravenous trastuzumab. Total trastuzumab clearance increases with decreasing concentrations due to parallel linear and non-linear elimination pathways.

Although the average trastuzumab exposure was higher following the first cycle in breast cancer patients receiving the once every three week schedule compared to the weekly schedule of trastuzumab, the average steady-state exposure was essentially the same at both dosages. The average trastuzumab exposure following the first cycle and at steady state as well as the time to steady state was higher in breast cancer patients compared to MGC patients at the same dosage; however, the reason for this exposure difference is unknown. Additional predicted trastuzumab exposure and PK parameters following the first trastuzumab cycle and at steady state exposure are described in Tables 7 and 8, respectively.

Population PK based simulations indicate that following discontinuation of trastuzumab, concentrations in at least 95% of breast cancer and MGC patients will decrease to approximately 3% of the population predicted steady-state trough serum concentration (approximately 97% washout) by 7 months [see Warnings and Precautions (5.1) and Use in Specific Populations (8.1, 8.3)].

Table 7 Population Predicted Cycle 1 PK Exposures (Median with 5th – 95th Percentiles) in Breast Cancer and MGC Patients
Schedule | Primary tumor type | N | Cmin (µg/mL) | Cmax (µg/mL) | AUC0-21days (µg.day/mL)
8 mg/kg + 6 mg/kg q3w | Breast cancer | 1195 | 29.4 (5.8 - 59.5) | 178 (117 - 291) | 1373 (736 - 2245)
8 mg/kg + 6 mg/kg q3w | MGC | 274 | 23.1 (6.1 - 50.3) | 132 (84.2 - 225) | 1109 (588 - 1938)
4 mg/kg + 2 mg/kg qw | Breast cancer | 1195 | 37.7 (12.3 - 70.9) | 88.3 (58 - 144) | 1066 (586 - 1754)

Table 8 Population Predicted Steady State PK Exposures (Median with 5th - 95th Percentiles) in Breast Cancer and MGC Patients
Schedule | Primary tumor type | N | Cmin,ssa (µg/mL) | Cmax,ssb (µg/mL) | AUCss, 0-21 days (µg.day/mL) | Time to steady-state (week) | Total CL range at steady-state (L/day)
8 mg/kg + 6 mg/kg q3w | Breast cancer | 1195 | 47.4 (5 - 115) | 179 (107 - 309) | 1794 (673 - 3618) | 12 | 0.173 - 0.283
8 mg/kg + 6 mg/kg q3w | MGC | 274 | 32.9 (6.1 - 88.9) | 131 (72.5 - 251) | 1338 (557 - 2875) | 9 | 0.189 - 0.337
4 mg/kg + 2 mg/kg qw | Breast cancer | 1195 | 66.1 (14.9 - 142) | 109 (51.0 - 209) | 1765 (647 - 3578) | 12 | 0.201 - 0.244

aSteady-state trough serum concentration of trastuzumab
bMaximum steady-state serum concentration of trastuzumab

Specific Populations

Based on a population pharmacokinetic analysis, no clinically significant differences were observed in the pharmacokinetics of trastuzumab based on age (< 65 (n = 1294); ≥ 65 (n = 288)), race (Asian (n = 264); non-Asian (n = 1324)) and renal impairment (mild (creatinine clearance [CLcr] 60 to 90 mL/min) (n = 636) or moderate (CLcr 30 to 60 mL/min) (n = 133)). The pharmacokinetics of trastuzumab products in patients with severe renal impairment, end-stage renal disease with or without hemodialysis, or hepatic impairment is unknown.

Drug Interaction Studies

There have been no formal drug interaction studies performed with trastuzumab products in humans. Clinically significant interactions between trastuzumab and concomitant medications used in clinical trials have not been observed.

Paclitaxel and doxorubicin: Concentrations of paclitaxel and doxorubicin and their major metabolites (i.e., 6-α hydroxyl-paclitaxel [POH], and doxorubicinol [DOL], respectively) were not altered in the presence of trastuzumab when used as combination therapy in clinical trials.
Trastuzumab concentrations were not altered as part of this combination therapy

Docetaxel and carboplatin: When trastuzumab was administered in combination with docetaxel or carboplatin, neither the plasma concentrations of docetaxel or carboplatin nor the plasma concentrations of trastuzumab were altered.

Cisplatin and capecitabine: In a drug interaction substudy conducted in patients in ToGA, the pharmacokinetics of cisplatin, capecitabine and their metabolites were not altered when administered in combination with trastuzumab

12.6 Immunogenicity

The observed incidence of anti-drug antibodies is highly dependent on the sensitivity and specificity of the assay. Differences in assay methods preclude meaningful comparisons of the incidence of anti-drug antibodies in the studies described below with the incidence of anti-drug antibodies in other studies, including those of trastuzumab or of other trastuzumab products.

Among 903 women with metastatic breast cancer, human anti human antibody (HAHA) to trastuzumab was detected in one patient using an enzyme linked immunosorbent assay (ELISA). This patient did not experience an allergic reaction. Samples for assessment of HAHA were not collected in studies of adjuvant breast cancer.

The clinical relevance of the development of anti-trastuzumab antibodies after treatment with trastuzumab is not known.

13 NONCLINICAL TOXICOLOGY

13.1 Carcinogenesis, Mutagenesis, Impairment of Fertility

Trastuzumab products have not been tested for carcinogenic potential.

No evidence of mutagenic activity was observed when trastuzumab was tested in the standard Ames bacterial and human peripheral blood lymphocyte mutagenicity assays at concentrations of up to 5000 mcg/mL. In an in vivo micronucleus assay, no evidence of chromosomal damage to mouse bone marrow cells was observed following bolus intravenous doses of up to 118 mg/kg of trastuzumab.

A fertility study was conducted in female cynomolgus monkeys at doses up to 25 times the weekly recommended human dose of 2 mg/kg of trastuzumab and has revealed no evidence of impaired fertility, as measured by menstrual cycle duration and female sex hormone levels.

14 CLINICAL STUDIES

14.1 Adjuvant Breast Cancer

The safety and efficacy of trastuzumab in women receiving adjuvant chemotherapy for HER2 overexpressing breast cancer were evaluated in an integrated analysis of two randomized, open-label, clinical trials (NSABP B31 and NCCTG N9831) with a total of 4063 women at the protocol-specified final overall survival analysis, a third randomized, open-label, clinical trial (HERA) with a total of 3386 women at definitive Disease-Free Survival analysis for one-year trastuzumab treatment versus observation, and a fourth randomized, open-label clinical trial with a total of 3222 patients (BCIRG006).

NSABP B31 and NCCTG N9831
In NSABP B31 and NCCTG N9831, breast tumor specimens were required to show HER2 overexpression (3+ by IHC) or gene amplification (by FISH). HER2 testing was verified by a central laboratory prior to randomization (NCCTG N9831) or was required to be performed at a reference laboratory (NSABP B31). Patients with a history of active cardiac disease based on symptoms, abnormal electrocardiographic, radiologic, or left ventricular ejection fraction findings or uncontrolled hypertension (diastolic  100 mm Hg or systolic  200 mm Hg) were not eligible.

Patients were randomized (1:1) to receive doxorubicin and cyclophosphamide followed by paclitaxel (AC paclitaxel) alone or paclitaxel plus trastuzumab (AC paclitaxel + trastuzumab). In both trials, patients received four 21-day cycles of doxorubicin 60 mg/m2 and cyclophosphamide 600 mg/m2. Paclitaxel was administered either weekly (80 mg/m2) or every 3 weeks (175 mg/m2) for a total of 12 weeks in NSABP B31; paclitaxel was administered only by the weekly schedule in NCCTG N9831. Trastuzumab was administered at 4 mg/kg on the day of initiation of paclitaxel and then at a dose of 2 mg/kg weekly for a total of 52 weeks. Trastuzumab treatment was permanently discontinued in patients who developed congestive heart failure, or persistent/recurrent LVEF decline [see Dosage and Administration (2.5)]. Radiation therapy, if administered, was initiated after the completion of chemotherapy. Patients with ER+ and/or PR+ tumors received hormonal therapy. The major efficacy outcome measure of the combined efficacy analysis was Disease-Free Survival (DFS), defined as the time from randomization to recurrence, occurrence of contralateral breast cancer, other second primary cancer, or death. An additional efficacy outcome measure was overall survival (OS).

A total of 3752 patients were included in the joint efficacy analysis of DFS following a median follow-up of 2.0 years in the AC paclitaxel + trastuzumab arm. The pre-planned final OS analysis from the joint analysis included 4063 patients and was performed when 707 deaths had occurred after a median follow-up of 8.3 years in the AC paclitaxel + trastuzumab arm. The data from both arms in NSABP B31 and two of the three study arms in NCCTG N9831 were pooled for efficacy analyses.

The patients included in the DFS analysis had a median age of 49 years (range, 2280 years; 6%
 65 years), 84% were white, 7% black, 4% Hispanic, and 4% Asian/Pacific Islander. Disease characteristics included 90% infiltrating ductal histology, 38% T1, 91% nodal involvement, 27% intermediate and 66% high grade pathology, and 53% ER+ and/or PR+ tumors.

HERA
In HERA, breast tumor specimens were required to show HER2 overexpression (3+ by IHC) or gene amplification (by FISH) as determined at a central laboratory. Patients with node-negative disease were required to have ≥ T1c primary tumor. Patients with a history of congestive heart failure or LVEF < 55%, uncontrolled arrhythmias, angina requiring medication, clinically significant valvular heart disease, evidence of transmural infarction on ECG, poorly controlled hypertension (systolic > 180 mm Hg or diastolic > 100 mm Hg) were not eligible.

Patients were randomized (1:1:1) upon completion of definitive surgery, and at least four cycles of chemotherapy to receive no additional treatment, or one year of trastuzumab treatment or two years of trastuzumab treatment. Patients undergoing a lumpectomy had also completed standard radiotherapy. Patients with ER+ and/or PgR+ disease received systemic adjuvant hormonal therapy at investigator discretion. Trastuzumab was administered with an initial dose of 8 mg/kg followed by subsequent doses of 6 mg/kg once every three weeks. The major efficacy outcome measure was Disease-Free Survival (DFS), defined as in NSABP B31 and NCCTG N9831.

HERA was designed to compare one and two years of once every three-week trastuzumab treatment versus observation in patients with HER2 positive EBC following surgery, established chemotherapy and radiotherapy (if applicable). A protocol specified interim efficacy analysis comparing one-year trastuzumab treatment to observation was performed at a median follow-up duration of 12.6 months in the trastuzumab arm.

Among the 3386 patients randomized to the observation (n = 1693) and trastuzumab one-year (n = 1693) treatment arms, the median age was 49 years (range 2180), 83% were White, and 13% were Asian. Disease characteristics: 94% infiltrating ductal carcinoma, 50% ER+ and/or PgR+, 57% node positive, 32% node negative, and in 11% of patients, nodal status was not assessable due to prior neo-adjuvant chemotherapy. Ninety-six percent (1055/1098) of patients with node-negative disease had high-risk features: among the 1098 patients with node-negative disease, 49% (543) were ER and PgR, and 47% (512) were ER and/or PgR and had at least one of the following high-risk features: pathological tumor size greater than 2 cm, Grade 23, or age  35 years. Prior to randomization, 94% of patients had received anthracycline-based chemotherapy regimens.

After the DFS results comparing observation to one-year trastuzumab treatment were disclosed, a prospectively planned analysis that included comparison of one year versus two years of trastuzumab treatment at a median follow-up duration of 8 years was performed. Based on this analysis, extending trastuzumab treatment for a duration of two years did not show additional benefit over treatment for one year [Hazard Ratios of two-years trastuzumab versus one-year trastuzumab treatment in the intent to treat (ITT) population for Disease-Free Survival (DFS) = 0.99 (95% CI: 0.87, 1.13), p-value = 0.90 and Overall Survival (OS) = 0.98 (0.83, 1.15); p-value = 0.78].

BCIRG006
In BCIRG006, breast tumor specimens were required to show HER2 gene amplification (FISH+ only) as determined at a central laboratory. Patients were required to have either node-positive disease, or node-negative disease with at least one of the following high-risk features:
ER/PR-negative, tumor size > 2 cm, age < 35 years, or histologic and/or nuclear Grade 2 or 3. Patients with a history of CHF, myocardial infarction, Grade 3 or 4 cardiac arrhythmia, angina requiring medication, clinically significant valvular heart disease, poorly controlled hypertension (diastolic > 100 mm Hg), any T4 or N2, or known N3 or M1 breast cancer were not eligible.

Patients were randomized (1:1:1) to receive doxorubicin and cyclophosphamide followed by docetaxel (AC-T), doxorubicin and cyclophosphamide followed by docetaxel plus trastuzumab (AC-TH), or docetaxel and carboplatin plus trastuzumab (TCH). In both the AC-T and AC-TH arms, doxorubicin 60 mg/m2 and cyclophosphamide 600 mg/m2 were administered every 3 weeks for four cycles; docetaxel 100 mg/m2 was administered every 3 weeks for four cycles. In the TCH arm, docetaxel 75 mg/m2 and carboplatin (at a target AUC of 6 mg/mL/min as a 30- to 60-minute infusion) were administered every 3 weeks for six cycles. Trastuzumab was administered weekly (initial dose of 4 mg/kg followed by weekly dose of 2 mg/kg) concurrently with either T or TC, and then every 3 weeks (6 mg/kg) as monotherapy for a total of 52 weeks. Radiation therapy, if administered, was initiated after completion of chemotherapy. Patients with ER+ and/or PR+ tumors received hormonal therapy. Disease-Free Survival (DFS) was the major efficacy outcome measure.

Among 3222 patients, the median age was 49 (range 22 to 74 years; 6%  65 years). Disease characteristics included 54% ER+ and/or PR+ and 71% node positive. Prior to randomization, all patients underwent primary surgery for breast cancer.

The results for DFS for the integrated analysis of NSABP B31 and NCCTG N9831, HERA, and BCIRG006 and OS results for the integrated analysis of NSABP B31 and NCCTG N9831, and HERA are presented in Table 9. For NSABP B31 and NCCTG N9831, the duration of DFS following a median follow-up of 2.0 years in the ACTH arm is presented in Figure 4, and the duration of OS after a median follow-up of 8.3 years in the ACTH arm is presented in Figure 5. The duration of DFS for BCIRG006 is presented in Figure 6. For NSABP B31 and NCCTG N9831, the OS hazard ratio was 0.64 (95% CI: 0.55, 0.74). At 8.3 years of median follow-up [ACTH], the survival rate was estimated to be 86.9% in the ACTH arm and 79.4% in the ACT arm. The final OS analysis results from NSABP B31 and NCCTG N9831 indicate that OS benefit by age, hormone receptor status, number of positive lymph nodes, tumor size and grade, and surgery/radiation therapy was consistent with the treatment effect in the overall population. In patients ≤ 50 years of age (n = 2197), the OS hazard ratio was 0.65 (95% CI: 0.52, 0.81) and in patients > 50 years of age (n = 1866), the OS hazard ratio was 0.63 (95% CI: 0.51, 0.78). In the subgroup of patients with hormone receptor-positive disease (ER-positive and/or PR-positive) (n = 2223), the hazard ratio for OS was 0.63 (95% CI: 0.51, 0.78). In the subgroup of patients with hormone receptor-negative disease (ER-negative and PR-negative) (n = 1830), the hazard ratio for OS was 0.64 (95% CI: 0.52, 0.80). In the subgroup of patients with tumor size ≤ 2 cm (n = 1604), the hazard ratio for OS was 0.52 (95% CI: 0.39, 0.71). In the subgroup of patients with tumor size > 2 cm (n = 2448), the hazard ratio for OS was 0.67 (95% CI: 0.56, 0.80).

Table 9: Efficacy Results from Adjuvant Treatment of Breast Cancer (NSABP B31 and NCCTG N9831, HERA, and BCIRG006)
 | DFS events | DFS Hazard ratio (95% CI) p-value | Deaths (OS events) | OS Hazard ratio p-value
NSABP B31 and NCCTG N9831a
AC→TH (n = 1872)b (n = 2031)c | 133b | 0.48b,d (0.39, 0.59) p< 0.0001e | 289c | 0.64c,d (0.55, 0.74) p< 0.0001e
AC→T (n = 1880)b (n = 2032)c | 261b |  | 418c
HERAf
Chemo→ Trastuzumab (n = 1693) | 127 | 0.54 (0.44, 0.67) p< 0.0001g | 31 | 0.75 p = NSh
Chemo→ Observation (n = 1693) | 219 |  | 40
BCIRG006i
TCH (n = 1075) | 134 | 0.67 (0.54 – 0.84) p=0.0006e,j | 56
AC→TH (n = 1074) | 121 | 0.60 (0.48 – 0.76) p< 0.0001e,j | 49
AC→T (n = 1073) | 180 |  | 80

CI = confidence interval.
a NSABP B31 and NCCTG N9831 regimens: doxorubicin and cyclophosphamide followed by paclitaxel (AC→T) or paclitaxel plus trastuzumab (AC→TH).
b Efficacy evaluable population, for the primary DFS analysis, following a median follow-up of 2.0 years in the AC→TH arm.
c Efficacy evaluable population, for the final OS analysis, following 707 deaths (8.3 years of median follow-up in the AC→TH arm).
d Hazard ratio estimated by Cox regression stratified by clinical trial, intended paclitaxel schedule, number of positive nodes, and hormone receptor status.
e stratified log-rank test.
f At definitive DFS analysis with median duration of follow-up of 12.6 months in the one- year trastuzumab treatment arm.
g log-rank test.
h NS = non-significant.
i BCIRG006 regimens: doxorubicin and cyclophosphamide followed by docetaxel (AC→T) or docetaxel plus trastuzumab (AC→TH); docetaxel and carboplatin plus trastuzumab (TCH).
j A two-sided alpha level of 0.025 for each comparison.

Figure 4:Duration of Disease-Free Survival in Patients with Adjuvant Treatment of Breast Cancer (NSABP B31 and NCCTG N9831)

Figure 5

Overall Survival in Patients with
Adjuvant Treatment of Breast Cancer (NSABP B31 and NCCTG N9831)

Figure 6
Disease-Free Survival in Patients with Adjuvant Treatment of Breast Cancer (BCIRG006)

Exploratory analyses of DFS as a function of HER2 overexpression or gene amplification were conducted for patients in Studies 2 and 3, where central laboratory testing data were available. The results are shown in Table 10. The number of events in NCCTG N9831 was small with the exception of the IHC 3+/FISH+ subgroup, which constituted 81% of those with data. Definitive conclusions cannot be drawn regarding efficacy within other subgroups due to the small number of events. The number of events in HERA was adequate to demonstrate significant effects on DFS in the IHC 3+/FISH unknown and the FISH+/IHC unknown subgroups.

Table 10: DFS in NCCTG N9831 and HERA for Patients with HER2 Overexpression or Amplification
 | NCCTG N9831 |  | HERAc
HER2 Assay Resulta | Number of Patients | Hazard Ratio DFS (95% CI) | Number of Patients | Hazard Ratio DFS (95% CI)
IHC 3+
FISH (+) | 1170 | 0.42 (0.27, 0.64) | 91 | 0.56 (0.13, 2.50)
FISH (−) | 51 | 0.71 (0.04, 11.79) | 8 | —
FISH Unknown | 51 | 0.69 (0.09, 5.14) | 2258 | 0.53 (0.41, 0.69)
IHC < 3+ / FISH (+) | 174 | 1.01 (0.18, 5.65) | 299b | 0.53 (0.20, 1.42)
IHC unknown / FISH (+) | — | — | 724 | 0.59 (0.38, 0.93)

aIHC by HercepTest, FISH by PathVysion (HER2/CEP17 ratio ≥ 2.0) as performed at a central laboratory.
b All cases in this category in HERA were IHC 2+.
cMedian follow-up duration of 12.6 months in the one-year trastuzumab treatment arm.

14.2 Metastatic Breast Cancer

The safety and efficacy of trastuzumab in treatment of women with metastatic breast cancer were studied in a randomized, controlled clinical trial in combination with chemotherapy (H0648g, n = 469 patients) and an open-label, single agent clinical trial (H0649g, n = 222 patients). Both trials studied patients with metastatic breast cancer whose tumors overexpress the HER2 protein. Patients were eligible if they had 2 or 3 levels of overexpression (based on a 0 to 3 scale) by immunohistochemical assessment of tumor tissue performed by a central testing lab.

Previously Untreated Metastatic Breast Cancer (H0648g)

H0648g was a multicenter, randomized, open-label clinical trial conducted in 469 women with metastatic breast cancer who had not been previously treated with chemotherapy for metastatic disease. Tumor specimens were tested by IHC (Clinical Trial Assay, CTA) and scored as 0, 1+, 2+, or 3+, with 3+ indicating the strongest positivity. Only patients with 2+ or 3+ positive tumors were eligible (about 33% of those screened). Patients were randomized to receive chemotherapy alone or in combination with trastuzumab given intravenously as a 4 mg/kg loading dose followed by weekly doses of trastuzumab at 2 mg/kg. For those who had received prior anthracycline therapy in the adjuvant setting, chemotherapy consisted of paclitaxel (175 mg/m2 over 3 hours every 21 days for at least six cycles); for all other patients, chemotherapy consisted of anthracycline plus cyclophosphamide (AC: doxorubicin 60 mg/m2 or epirubicin 75 mg/m2 plus 600 mg/m2 cyclophosphamide every 21 days for six cycles). Sixty-five percent of patients randomized to receive chemotherapy alone in this study received trastuzumab at the time of disease progression as part of a separate extension study.

Based upon the determination by an independent Response Evaluation Committee, the patients randomized to trastuzumab and chemotherapy experienced a significantly longer median time to disease progression (TTP), a higher overall response rate (ORR), and a longer median duration of response (DoR) as compared with patients randomized to chemotherapy alone. Patients randomized to trastuzumab and chemotherapy also had a longer median overall survival (OS) (see Table 11). These treatment effects were observed both in patients who received trastuzumab plus paclitaxel and in those who received trastuzumab plus AC; however, the magnitude of the effects was greater in the paclitaxel subgroup.

Table 11: H0648g: Efficacy Results in First-Line Treatment for Metastatic Breast Cancer
 | Combined Results |  | Paclitaxel Subgroup |  | ACaSubgroup
 | Trastuzumab + All Chemotherapy (n = 235) | All Chemotherapy (n = 234) | Trastuzumab + Paclitaxel (n = 92) | Paclitaxel (n = 96) | Trastuzumab + ACa (n = 143) | ACa (n = 138)
Time to Disease Progression (TTP)
Median; (months)b,c | 7.2 | 4.5 | 6.7 | 2.5 | 7.6 | 5.7
95% CI | 7, 8 | 4, 5 | 5, 10 | 2, 4 | 7, 9 | 5, 7
p-valued | < 0.0001 |  | < 0.0001 |  | 0.002
Overall Response Rate (ORR)b
Events (n) | 45 | 29 | 38 | 15 | 50 | 38
95% CI | 39, 51 | 23, 35 | 28, 48 | 8, 22 | 42, 58 | 30, 46
p-valuee | < 0.001 |  | < 0.001 |  | 0.10
Duration of Response (DoR)
Median (months)b,c | 8.3 | 5.8 | 8.3 | 4.3 | 8.4 | 6.4
25%, 75% Quartile | 6, 15 | 4, 8 | 5 ,11 | 4, 7 | 6, 15 | 4, 8
Overall Survival (OS)
Median (months)c | 25.1 | 20.3 | 22.1 | 18.4 | 26.8 | 21.4
95% CI | 22, 30 | 17, 24 | 17, 29 | 13, 24 | 23, 33 | 18, 27
p-valued | 0.05 |  | 0.17 |  | 0.16

aAC = Anthracycline (doxorubicin or epirubicin) and cyclophosphamide.
bAssessed by an independent Response Evaluation Committee.
cKaplan-Meier Estimate.
dlog-rank test.
eχ2-test.

Data from H0648g suggest that the beneficial treatment effects were largely limited to patients with the highest level of HER2 protein overexpression (3+) (see Table 12).

Table 12: Treatment Effects in H0648g as a Function of HER2 Overexpression or Amplification
HER2 Assay Result | Number of Patients (N) | Relative Riskbfor Time to Disease Progression (95% CI) | Relative Riskbfor Mortality (95% CI)
CTA 2+ or 3+ | 469 | 0.49 (0.40, 0.61) | 0.80 (0.64, 1.00)
FISH (+)a | 325 | 0.44 (0.34, 0.57) | 0.70 (0.53, 0.91)
FISH (−)a | 126 | 0.62 (0.42, 0.94) | 1.06 (0.70, 1.63)
CTA 2+ | 120 | 0.76 (0.50, 1.15) | 1.26 (0.82, 1.94)
FISH (+) | 32 | 0.54 (0.21, 1.35) | 1.31 (0.53, 3.27)
FISH (–) | 83 | 0.77 (0.48, 1.25) | 1.11 (0.68, 1.82)
CTA 3+ | 349 | 0.42 (0.33, 0.54) | 0.70 (0.51, 0.90)
FISH (+) | 293 | 0.42 (0.32, 0.55) | 0.67 (0.51, 0.89)
FISH (–) | 43 | 0.43 (0.20, 0.94) | 0.88 (0.39, 1.98)

aFISH testing results were available for 451 of the 469 patients enrolled on study.
bThe relative risk represents the risk of progression or death in the trastuzumab plus chemotherapy arm versus the chemotherapy arm.

Previously Treated Metastatic Breast Cancer (H0649g)

Trastuzumab was studied as a single agent in a multicenter, open-label, single-arm clinical trial (H0649g) in patients with HER2 overexpressing metastatic breast cancer who had relapsed following one or two prior chemotherapy regimens for metastatic disease. Of 222 patients enrolled, 66% had received prior adjuvant chemotherapy, 68% had received two prior chemotherapy regimens for metastatic disease, and 25% had received prior myeloablative treatment with hematopoietic rescue. Patients were treated with a loading dose of 4 mg/kg IV followed by weekly doses of trastuzumab at 2 mg/kg IV.

The ORR (complete response  partial response), as determined by an independent Response Evaluation Committee, was 14%, with a 2% complete response rate and a 12% partial response rate. Complete responses were observed only in patients with disease limited to skin and lymph nodes. The overall response rate in patients whose tumors tested as CTA 3+ was 18% while in those that tested as CTA 2+, it was 6%.

14.3 Metastatic Gastric Cancer

The safety and efficacy of trastuzumab in combination with cisplatin and a fluoropyrimidine (capecitabine or 5-fluorouracil) were studied in patients previously untreated for metastatic gastric or gastroesophageal junction adenocarcinoma (ToGA). In this open-label, multi-center trial, 594 patients were randomized 1:1 to trastuzumab in combination with cisplatin and a fluoropyrimidine (FC+H) or chemotherapy alone (FC). Randomization was stratified by extent of disease (metastatic vs. locally advanced), primary site (gastric vs. gastroesophageal junction), tumor measurability (yes vs. no), ECOG performance status (0, 1 vs. 2), and fluoropyrimidine (capecitabine vs. 5-fluorouracil). All patients were either HER2 gene amplified (FISH+) or HER2 overexpressing (IHC 3+). Patients were also required to have adequate cardiac function (e.g., LVEF > 50%).

On the trastuzumab-containing arm, trastuzumab was administered as an IV infusion at an initial dose of 8 mg/kg followed by 6 mg/kg every 3 weeks until disease progression. On both study arms cisplatin was administered at a dose of 80 mg/m2 Day 1 every 3 weeks for 6 cycles as a 2 hour IV infusion. On both study arms, capecitabine was administered at 1000 mg/m2 dose orally twice daily (total daily dose 2000 mg/m2) for 14 days of each 21 day cycle for 6 cycles. Alternatively, continuous intravenous infusion (CIV) 5-fluorouracil was administered at a dose of 800 mg/m2/day from Day 1 through Day 5 every three weeks for 6 cycles.

The median age of the study population was 60 years (range: 2183); 76% were male; 53% were Asian, 38% Caucasian, 5% Hispanic, 5% other racial/ethnic groups; 91% had ECOG PS of 0 or 1; 82% had primary gastric cancer and 18% had primary gastroesophageal adenocarcinoma. Of these patients, 23% had undergone prior gastrectomy, 7% had received prior neoadjuvant and/or adjuvant therapy, and 2% had received prior radiotherapy.

The main outcome measure of ToGA was overall survival (OS), analyzed by the unstratified log-rank test. The final OS analysis based on 351 deaths was statistically significant (nominal significance level of 0.0193). An updated OS analysis was conducted at one year after the final analysis. The efficacy results of both the final and the updated analyses are summarized in Table 13 and Figure 7.

Table 13: Study 7: Overall Survival in ToGA (ITT Population)
 | FCa+ Trastuzumab Arm N = 298 |  | FCaArm N = 296
Overall Survival (interim analysis)
N (%) | 167 (56.0%) |  | 184 (62.2%)
Median (months) | 13.5 |  | 11.0
95% CI | (11.7, 15.7) |  | (9.4, 12.5)
Hazard Ratio | 0.73
95% CI | (0.60, 0.91)
p-valueb | 0.0038
Overall Survival (updated)
N (%) | 221 (74.2%) |  | 227 (76.7%)
Median (months) | 13.1 |  | 11.7
95% CI | (11.9, 15.1) |  | (10.3, 13.0)
Hazard Ratio | 0.80
95% CI | (0.67, 0.97)

Figure 7: Updated Overall Survival in Patients with Metastatic Gastric Cancer (ToGA)

An exploratory analysis of OS in patients based on HER2 gene amplification (FISH) and protein overexpression (IHC) testing is summarized in Table 14.

Table 14: Exploratory Analyses by HER2 Status Using Updated Overall Survival Results
 | FC (N = 296)a | FC + H (N = 298)b
FISH+ / IHC 0, 1+ subgroup (N=133)
No. Deaths / n (%) | 57/71 (80%) | 56/62 (90%)
Median OS Duration (mos.) | 8.8 | 8.3
95% CI (mos.) | (6.4, 11.7) | (6.2, 10.7)
Hazard ratio (95% CI) | 1.33 (0.92, 1.92)
FISH+ / IHC2+ subgroup (N=160)
No. Deaths / n (%) | 65/80 (81%) | 64/80 (80%)
Median OS Duration (mos.) | 10.8 | 12.3
95% CI (mos.) | (6.8, 12.8) | (9.5, 15.7)
Hazard ratio (95% CI) | 0.78 (0.55, 1.10)
FISH+ or FISH- / IHC3+csubgroup (N=294)
No. Deaths / n (%) | 104/143 (73%) | 96/151 (64%)
Median OS Duration (mos.) | 13.2 | 18.0
95% CI (mos.) | (11.5, 15.2) | (15.5, 21.2)
Hazard ratio (95% CI) | 0.66 (0.50, 0.87)

aTwo patients on the FC arm who were FISH+ but IHC status unknown were excluded from the exploratory subgroup analyses.
bFive patients on the trastuzumab-containing arm who were FISH+, but IHC status unknown were excluded from the exploratory subgroup analyses.
cIncludes 6 patients on chemotherapy arm, 10 patients on trastuzumab arm with FISH–, IHC3+ and 8 patients on chemotherapy arm, 8 patients on trastuzumab arm with FISH status unknown, IHC 3+.

16 HOW SUPPLIED/STORAGE AND HANDLING

STORAGE AND HANDLING

420 mg Multiple-dose vial
HERCESSITM(trastuzumab-strf) for injection 420 mg/vial is supplied in a multiple-dose vial as a white to pale yellow lyophilized sterile powder with a cake-like appearance, under vacuum. Each carton contains one multiple-dose vial of HERCESSITM.
NDC 69448-016-11.

150 mg Single-dose vial
HERCESSITM(trastuzumab-strf) for injection 150 mg/vial i s supplied in a single-dose vial as a preservative-free, white to pale yellow lyophilized sterile powder with a cake-like appearance, under vacuum. Each carton contains one single-dose vial of HERCESSITM.
NDC 69448-015-05.

Store HERCESSITMvials refrigerated at 2°C to 8°C (36°F to 46°F) in the original carton until time of reconstitution. Do not freeze. Do not shake

17 PATIENT COUNSELING INFORMATION

Cardiomyopathy:
• Advise patients to contact a health care professional immediately for any of the following: new onset or worsening shortness of breath, cough, swelling of the ankles/legs, swelling of the face, palpitations, weight gain of more than 5 pounds in 24 hours, dizziness or loss of consciousness
[see Boxed Warning: Cardiomyopathy].

Embryo-Fetal Toxicity:
• Advise pregnant women and females of reproductive potential that HERCESSITMexposure during pregnancy or within 7 months prior to conception can result in fetal harm. Advise female patients to contact their healthcare provider with a known or suspected pregnancy [see Use in Specific Populations (8.1)].
• Advise females of reproductive potential to use effective contraception during treatment and for 7 months following the last dose of HERCESSITM [see Use in Specific Populations (8.3)].

HERCESSITM[trastuzumab-strf]
Manufactured at:
Shanghai Henlius Biologics Co., Ltd.
Building 1, No. 182 Wenjun Road, Songjiang District
Shanghai, China

Manufactured by:
Accord BioPharma Inc.
8041 Arco Corporate Drive, Suite 200,
Raleigh, NC, 27617 USA
U.S. License No. 2105
HERCESSITMis a trademark of Accord BioPharma Inc.

PRINCIPAL DISPLAY PANEL - container-label

NDC 69448-015-05